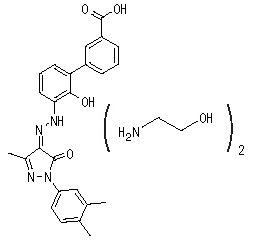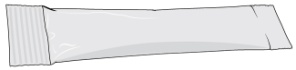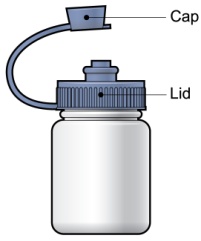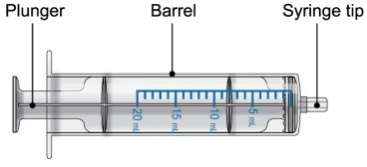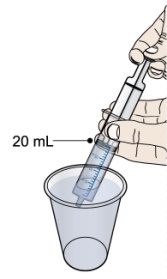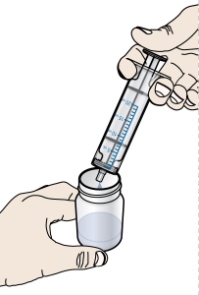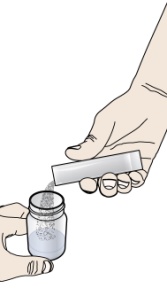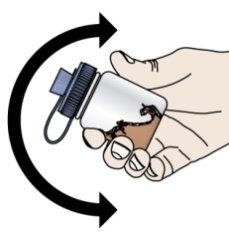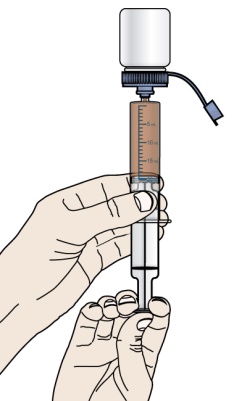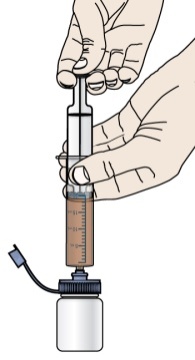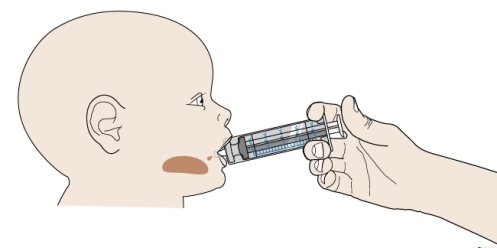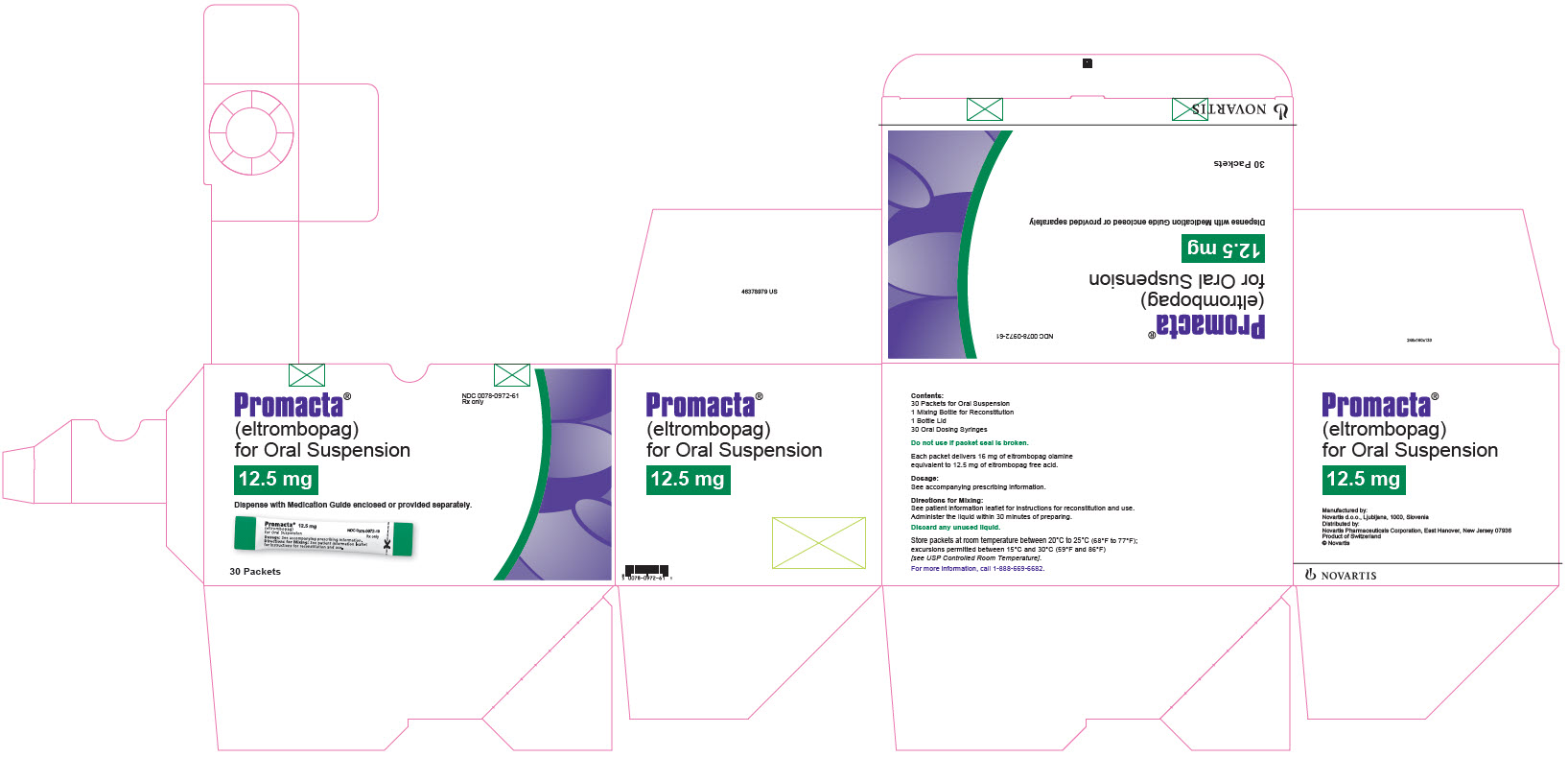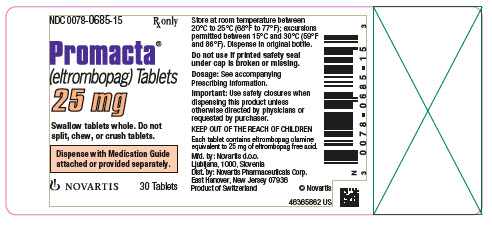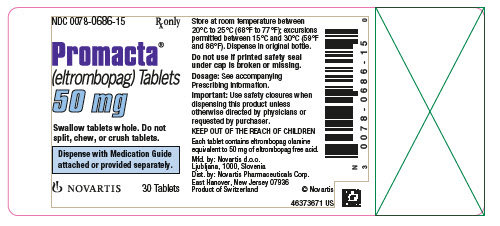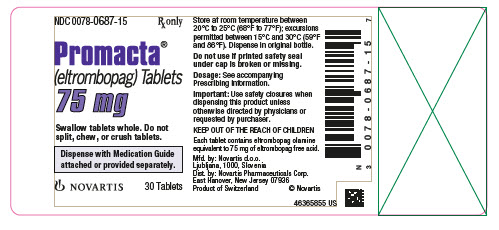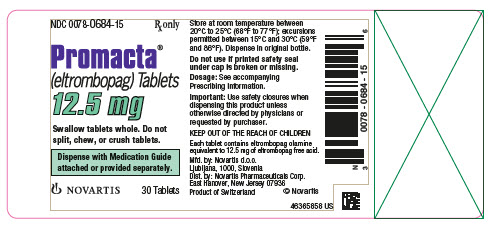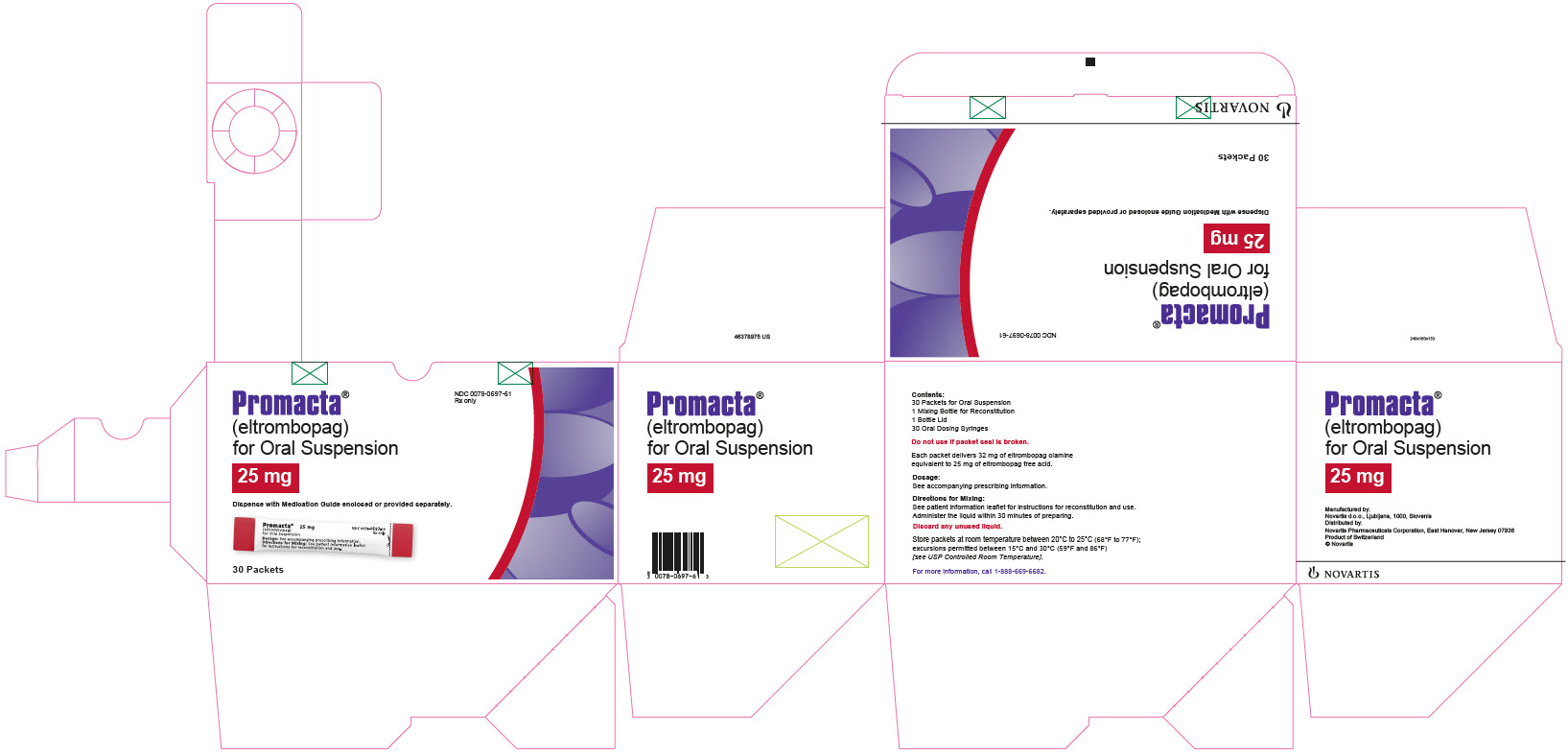 DRUG LABEL: PROMACTA
NDC: 0078-0684 | Form: TABLET, FILM COATED
Manufacturer: Novartis Pharmaceuticals Corporation
Category: prescription | Type: HUMAN PRESCRIPTION DRUG LABEL
Date: 20251218

ACTIVE INGREDIENTS: ELTROMBOPAG OLAMINE 12.5 mg/1 1
INACTIVE INGREDIENTS: MAGNESIUM STEARATE; MANNITOL; CELLULOSE, MICROCRYSTALLINE; POVIDONE; SODIUM STARCH GLYCOLATE TYPE A POTATO; HYPROMELLOSES; POLYETHYLENE GLYCOL 400; TITANIUM DIOXIDE; FERRIC OXIDE RED; FERROSOFERRIC OXIDE

HIGHLIGHTS OF PRESCRIBING INFORMATION

These highlights do not include all the information needed to use PROMACTA safely and effectively. See full prescribing information for PROMACTA.
PROMACTA® (eltrombopag) tablets, for oral use
PROMACTA® (eltrombopag) for oral suspension
Initial U.S. Approval: 2008

WARNING: RISK FOR HEPATIC DECOMPENSATION IN PATIENTS WITH CHRONIC HEPATITIS C and RISK OF HEPATOTOXICITY

See full prescribing information for complete boxed warning.

In patients with chronic hepatitis C, PROMACTA in combination with interferon and ribavirin may increase the risk of hepatic decompensation. (5.1)

PROMACTA may increase the risk of severe and potentially life-threatening hepatotoxicity. Monitor hepatic function and discontinue dosing as recommended. (5.2)

RECENT MAJOR CHANGES

Warnings and Precautions, Laboratory Test Interference (5.6) | 6/2025

1 INDICATIONS AND USAGE

PROMACTA is a thrombopoietin receptor agonist indicated:

- for the treatment of thrombocytopenia in adult and pediatric patients 1 year and older with persistent or chronic immune thrombocytopenia (ITP) who have had an insufficient response to corticosteroids, immunoglobulins, or splenectomy. PROMACTA should be used only in patients with ITP whose degree of thrombocytopenia and clinical condition increase the risk for bleeding. (1.1)
- for the treatment of thrombocytopenia in patients with chronic hepatitis C to allow the initiation and maintenance of interferon-based therapy. PROMACTA should be used only in patients with chronic hepatitis C whose degree of thrombocytopenia prevents the initiation of interferon-based therapy or limits the ability to maintain interferon-based therapy. (1.2)
- in combination with standard immunosuppressive therapy for the first-line treatment of adult and pediatric patients 2 years and older with severe aplastic anemia. (1.3)
- for the treatment of patients with severe aplastic anemia who have had an insufficient response to immunosuppressive therapy. (1.3)

Limitations of Use:

- PROMACTA is not indicated for the treatment of patients with myelodysplastic syndrome (MDS). (1.4)
- Safety and efficacy have not been established in combination with direct-acting antiviral agents used without interferon for treatment of chronic hepatitis C infection. (1.4)

2 DOSAGE AND ADMINISTRATION

- Take PROMACTA without a meal or with a meal low in calcium (≤ 50 mg). Take PROMACTA at least 2 hours before or 4 hours after any medications or products containing polyvalent cations, such as antacids, calcium-rich foods, and mineral supplements. (2.4, 7.1, 12.3)
- Persistent or Chronic ITP: Initiate PROMACTA at 50 mg orally once daily for most adult and pediatric patients 6 years and older, and at 25 mg orally once daily for pediatric patients aged 1 to 5 years. Dose reductions are needed for patients with hepatic impairment and some patients of East-/Southeast-Asian ancestry. Adjust to maintain platelet count greater than or equal to 50 x 10^9/L. Do not exceed 75 mg per day. (2.1, 8.6, 8.7)
- Chronic Hepatitis C-associated Thrombocytopenia: Initiate PROMACTA at 25 mg orally once daily for all patients. Adjust to achieve target platelet count required to initiate antiviral therapy. Do not exceed a daily dose of 100 mg. (2.2)
- First-line Severe Aplastic Anemia: Initiate PROMACTA orally once daily at 2.5 mg/kg (in pediatric patients aged 2 to 5 years old), 75 mg (pediatric patients aged 6 to 11 years old), or 150 mg for patients aged 12 years and older concurrently with standard immunosuppressive therapy. Reduce initial dose in patients of East-/Southeast-Asian ancestry. Modify dosage for toxicity or elevated platelet counts. (2.3, 8.7)
- Refractory Severe Aplastic Anemia: Initiate PROMACTA orally at 50 mg once daily. Reduce initial dose in patients with hepatic impairment or patients of East-/Southeast-Asian ancestry. Adjust to maintain platelet count greater than 50 x 10^9/L. Do not exceed 150 mg per day. (2.3, 8.6, 8.7)

3 DOSAGE FORMS AND STRENGTHS

- Tablets: 12.5 mg, 25 mg, 50 mg, and 75 mg (3)
- For oral suspension: 12.5 mg and 25 mg (3)

4 CONTRAINDICATIONS

None. (4)

5 WARNINGS AND PRECAUTIONS

- Hepatotoxicity: Monitor liver function before and during therapy. (5.2)
- Increased Risk of Death and Progression of Myelodysplastic Syndromes to Acute Myeloid Leukemia. (5.3)
- Thrombotic/Thromboembolic Complications: Portal vein thrombosis has been reported in patients with chronic liver disease receiving PROMACTA. Monitor platelet counts regularly. (5.4)

6 ADVERSE REACTIONS

Across all indications, the most common adverse reactions (≥ 20% in any indication) were: anemia, nausea, pyrexia, alanine aminotransferase increased, cough, fatigue, headache, and diarrhea. (6.1)

To report SUSPECTED ADVERSE REACTIONS, contact Novartis Pharmaceuticals Corporation at 1-888-669-6682 or FDA at 1-800-FDA-1088 or www.fda.gov/medwatch.

8 USE IN SPECIFIC POPULATIONS

- Lactation: Advise women not to breastfeed during treatment. (8.2)

FULL PRESCRIBING INFORMATION

WARNING: RISK FOR HEPATIC DECOMPENSATION IN PATIENTS WITH CHRONIC HEPATITIS C and RISK OF HEPATOTOXICITY

In patients with chronic hepatitis C, PROMACTA in combination with interferon and ribavirin may increase the risk of hepatic decompensation [see Warnings and Precautions (5.1)].

PROMACTA may increase the risk of severe and potentially life-threatening hepatotoxicity. Monitor hepatic function and discontinue dosing as recommended [see Warnings and Precautions (5.2)].

1 INDICATIONS AND USAGE

1.1 Treatment of Thrombocytopenia in Patients With Persistent or Chronic Immune Thrombocytopenia

PROMACTA is indicated for the treatment of thrombocytopenia in adult and pediatric patients 1 year and older with persistent or chronic immune thrombocytopenia (ITP) who have had an insufficient response to corticosteroids, immunoglobulins, or splenectomy. PROMACTA should be used only in patients with ITP whose degree of thrombocytopenia and clinical condition increase the risk for bleeding.

1.2 Treatment of Thrombocytopenia in Patients With Hepatitis C Infection

PROMACTA is indicated for the treatment of thrombocytopenia in patients with chronic hepatitis C to allow the initiation and maintenance of interferon-based therapy. PROMACTA should be used only in patients with chronic hepatitis C whose degree of thrombocytopenia prevents the initiation of interferon-based therapy or limits the ability to maintain interferon-based therapy.

1.3 Treatment of Severe Aplastic Anemia

- PROMACTA is indicated in combination with standard immunosuppressive therapy (IST) for the first-line treatment of adult and pediatric patients 2 years and older with severe aplastic anemia.
- PROMACTA is indicated for the treatment of patients with severe aplastic anemia who have had an insufficient response to immunosuppressive therapy.

1.4 Limitations of Use

- PROMACTA is not indicated for the treatment of patients with myelodysplastic syndromes (MDS) [see Warnings and Precautions (5.3)].
- Safety and efficacy have not been established in combination with direct-acting antiviral agents used without interferon for treatment of chronic hepatitis C infection.

2 DOSAGE AND ADMINISTRATION

2.1 Persistent or Chronic Immune Thrombocytopenia

Use the lowest dose of PROMACTA to achieve and maintain a platelet count greater than or equal to 50 x 10^9/L as necessary to reduce the risk for bleeding. Dose adjustments are based upon the platelet count response. Do not use PROMACTA to normalize platelet counts [see Warnings and Precautions (5.4)]. In clinical trials, platelet counts generally increased within 1 to 2 weeks after starting PROMACTA and decreased within 1 to 2 weeks after discontinuing PROMACTA [see Clinical Studies (14.1)].

Initial Dose Regimen:

Adult and Pediatric Patients 6 Years and Older with ITP: Initiate PROMACTA at a dose of 50 mg orally once daily, except in patients who are of East-/Southeast-Asian ancestry or who have mild to severe hepatic impairment (Child-Pugh class A, B, C).

For patients of East-/Southeast-Asian ancestry with ITP, initiate PROMACTA at a reduced dose of 25 mg orally once daily [see Use in Specific Populations (8.7), Clinical Pharmacology (12.3)].

For patients with ITP and mild, moderate, or severe hepatic impairment (Child-Pugh class A, B, C), initiate PROMACTA at a reduced dose of 25 mg orally once daily [see Use in Specific Populations (8.6), Clinical Pharmacology (12.3)].

For patients of East-/Southeast-Asian ancestry with ITP and hepatic impairment (Child-Pugh class A, B, C), consider initiating PROMACTA at a reduced dose of 12.5 mg orally once daily [see Clinical Pharmacology (12.3)].

Pediatric Patients with ITP Aged 1 to 5 Years: Initiate PROMACTA at a dose of 25 mg orally once daily [see Use in Specific Populations (8.7), Clinical Pharmacology (12.3)].

Monitoring and Dose Adjustment: After initiating PROMACTA, adjust the dose to achieve and maintain a platelet count greater than or equal to 50 x 10^9/L as necessary to reduce the risk for bleeding. Do not exceed a dose of 75 mg daily. Monitor clinical hematology and liver tests regularly throughout therapy with PROMACTA and modify the dosage regimen of PROMACTA based on platelet counts as outlined in Table 1. During therapy with PROMACTA, assess complete blood counts (CBCs) with differentials, including platelet counts, weekly until a stable platelet count has been achieved. Obtain CBCs with differentials, including platelet counts, monthly thereafter.

When switching between the oral suspension and tablet, assess platelet counts weekly for 2 weeks, and then follow standard monthly monitoring.

Table 1. Dose Adjustments of PROMACTA in Patients With Persistent or Chronic Immune Thrombocytopenia
Platelet count result | Dose adjustment or response
< 50 x 10^9/L following at least 2 weeks of PROMACTA | Increase daily dose by 25 mg to a maximum of 75 mg/day.; For patients taking 12.5 mg once daily, increase the dose to 25 mg daily before increasing the dose amount by 25 mg.
≥ 200 x 10^9/L to ≤ 400 x 10^9/L at any time | Decrease the daily dose by 25 mg. Wait 2 weeks to assess the effects of this and any subsequent dose adjustments.; For patients taking 25 mg once daily, decrease the dose to 12.5 mg once daily.
> 400 x 10^9/L | Stop PROMACTA; increase the frequency of platelet monitoring to twice weekly.; Once the platelet count is < 150 x 10^9/L, reinitiate therapy at a daily dose reduced by 25 mg.; For patients taking 25 mg once daily, reinitiate therapy at a daily dose of 12.5 mg.
> 400 x 10^9/L after 2 weeks of therapy at lowest dose of PROMACTA | Discontinue PROMACTA.

In patients with ITP and hepatic impairment (Child-Pugh class A, B, C), after initiating PROMACTA or after any subsequent dosing increase, wait 3 weeks before increasing the dose.

Modify the dosage regimen of concomitant ITP medications, as medically appropriate, to avoid excessive increases in platelet counts during therapy with PROMACTA. Do not administer more than one dose of PROMACTA within any 24-hour period.

Discontinuation: Discontinue PROMACTA if the platelet count does not increase to a level sufficient to avoid clinically important bleeding after 4 weeks of therapy with PROMACTA at the maximum daily dose of 75 mg. Excessive platelet count responses, as outlined in Table 1, or important liver test abnormalities (e.g., transaminases and/or bilirubin) also necessitate discontinuation of PROMACTA [see Warnings and Precautions (5.2, 5.6) and Drug Interactions (7.5)]. Obtain CBCs with differentials, including platelet counts, weekly for at least 4 weeks following discontinuation of PROMACTA.

2.2 Chronic Hepatitis C-Associated Thrombocytopenia

Use the lowest dose of PROMACTA to achieve and maintain a platelet count necessary to initiate and maintain antiviral therapy with pegylated interferon and ribavirin. Dose adjustments are based upon the platelet count response. Do not use PROMACTA to normalize platelet counts [see Warnings and Precautions (5.4)]. In clinical trials, platelet counts generally began to rise within the first week of treatment with PROMACTA [see Clinical Studies (14.2)].

Initial Dose Regimen: Initiate PROMACTA at a dose of 25 mg orally once daily.

Monitoring and Dose Adjustment: Adjust the dose of PROMACTA in 25 mg increments every 2 weeks as necessary to achieve the target platelet count required to initiate antiviral therapy. Monitor platelet counts every week prior to starting antiviral therapy.

During antiviral therapy, adjust the dose of PROMACTA to avoid dose reductions of peginterferon. Monitor CBCs with differentials, including platelet counts, weekly during antiviral therapy until a stable platelet count is achieved. Monitor platelet counts monthly thereafter. Do not exceed a dose of 100 mg daily. Monitor clinical hematology and liver tests (e.g., transaminases and bilirubin) regularly throughout therapy with PROMACTA [see Drug Interactions (7.5)].

For specific dosage instructions for peginterferon or ribavirin, refer to their respective prescribing information.

Table 2. Dose Adjustments of PROMACTA in Adults With Thrombocytopenia Due to Chronic Hepatitis C
Platelet count result | Dose adjustment or response
< 50 x 10^9/L following at least 2 weeks of PROMACTA | Increase daily dose by 25 mg to a maximum of 100 mg/day.
≥ 200 x 10^9/L to ≤ 400 x 10^9/L at any time | Decrease the daily dose by 25 mg.; Wait 2 weeks to assess the effects of this and any subsequent dose adjustments.
> 400 x 10^9/L | Stop PROMACTA; increase the frequency of platelet monitoring to twice weekly.; Once the platelet count is < 150 x 10^9/L, reinitiate therapy at a daily dose reduced by 25 mg.; For patients taking 25 mg once daily, reinitiate therapy at a daily dose of 12.5 mg.
> 400 x 10^9/L after 2 weeks of therapy at lowest dose of PROMACTA | Discontinue PROMACTA.

Discontinuation: The prescribing information for pegylated interferon and ribavirin include recommendations for antiviral treatment discontinuation for treatment futility. Refer to pegylated interferon and ribavirin prescribing information for discontinuation recommendations for antiviral treatment futility.

PROMACTA should be discontinued when antiviral therapy is discontinued. Excessive platelet count responses, as outlined in Table 2, or important liver test abnormalities also necessitate discontinuation of PROMACTA [see Warnings and Precautions (5.2)].

2.3 Severe Aplastic Anemia

First-Line Severe Aplastic Anemia

Initiate PROMACTA concurrently with standard immunosuppressive therapy [see Clinical Studies (14.3)].

Initial Dose Regimen

The recommended initial dose regimen is listed in Table 3. Do not exceed the initial dose of PROMACTA.

Table 3. Recommended Initial PROMACTA Dose Regimen in the First-Line Treatment of Severe Aplastic Anemia
Age | Dose regimen
Patients 12 years and older | 150 mg orally once daily for 6 months
Pediatric patients 6 to 11 years | 75 mg orally once daily for 6 months
Pediatric patients 2 to 5 years | 2.5 mg/kg orally once daily for 6 months

For patients with severe aplastic anemia of East-/Southeast-Asian ancestry or those with mild, moderate, or severe hepatic impairment (Child-Pugh class A, B, C), decrease the initial PROMACTA dose by 50% as listed in Table 4 [see Use in Specific Populations (8.6, 8.7), Clinical Pharmacology (12.3)].

If baseline alanine aminotransferase (ALT) or aspartate aminotransferase (AST) levels are > 6 x upper limit of normal (ULN), do not initiate PROMACTA until transaminase levels are < 5 x ULN. Determine the initial dose for these patients based on Table 3 or Table 4.

Table 4. Recommended Initial PROMACTA Dose Regimen for Patients of East-/Southeast-Asian Ancestry or Those With Mild, Moderate, or Severe Hepatic Impairment (Child-Pugh class A, B, C) in the First-Line Treatment of Severe Aplastic Anemia
Age | Dose regimen
Patients 12 years and older | 75 mg orally once daily for 6 months
Pediatric patients 6 to 11 years | 37.5 mg orally once daily for 6 months
Pediatric patients 2 to 5 years | 1.25 mg/kg orally once daily for 6 months

Monitoring and Dose Adjustment for PROMACTA: Perform clinical hematology and liver tests regularly throughout therapy with PROMACTA [see Warnings and Precautions (5.2)].

Modify the dosage regimen of PROMACTA based on platelet counts as outlined in Table 5.

Table 5. Dose Adjustments of PROMACTA for Elevated Platelet Counts in the First-Line Treatment of Severe Aplastic Anemia
Platelet count result | Dose adjustment or response
> 200 x 10^9/L to ≤ 400 x 10^9/L | Decrease the daily dose by 25 mg every 2 weeks to lowest dose that maintains platelet count ≥ 50 x 10^9/L. In pediatric patients under 12 years of age, decrease the dose by 12.5 mg.
> 400 x 10^9/L | Discontinue PROMACTA for one week. Once the platelet count is < 200 x 10^9/L, reinitiate PROMACTA at a daily dose reduced by 25 mg (or 12.5 mg in pediatric patients under 12 years of age).

Table 6 summarizes the recommendations for dose interruption, reduction, or discontinuation of PROMACTA in the management of elevated liver transaminase levels and thromboembolic events.

Table 6. Recommended Dose Modifications for PROMACTA for ALT or AST Elevations and Thromboembolic Events
Event | Recommendation
ALT or AST elevations | Increase in ALT or AST > 6 x ULN Discontinue PROMACTA. Once ALT or AST is < 5 x ULN, reinitiate PROMACTA at the same dose.; Increase in ALT or AST > 6 x ULN after reinitiating PROMACTA Discontinue PROMACTA and monitor ALT or AST at least every 3 to 4 days. Once ALT or AST is < 5 x ULN, reinitiate PROMACTA at a daily dose reduced by 25 mg compared to the previous dose.; If ALT or AST returns to > 6 x ULN on the reduced dose Reduce the daily dose of PROMACTA by 25 mg until ALT or AST is < 5 x ULN.; In pediatric patients under 12 years of age, reduce the daily dose by at least 15% to the nearest dose that can be administered.
Thromboembolic events (e.g., deep vein thrombosis, pulmonary embolus, stroke, myocardial infarction) | Discontinue PROMACTA but remain on horse antithymocyte globulin (h-ATG) and cyclosporine.
Abbreviations: ALT, alanine aminotransferase; AST, aspartate aminotransferase; ULN, upper limit of normal.

The total duration of PROMACTA treatment is 6 months.

Refractory Severe Aplastic Anemia

Use the lowest dose of PROMACTA to achieve and maintain a hematologic response. Dose adjustments are based upon the platelet count. Hematologic response requires dose titration, generally up to 150 mg, and may take up to 16 weeks after starting PROMACTA [see Clinical Studies (14.3)].

Initial Dose Regimen: Initiate PROMACTA at a dose of 50 mg orally once daily.

For patients with severe aplastic anemia of East-/Southeast-Asian ancestry or those with mild, moderate, or severe hepatic impairment (Child-Pugh class A, B, C), initiate PROMACTA at a reduced dose of 25 mg orally once daily [see Use in Specific Populations (8.6, 8.7), Clinical Pharmacology (12.3)].

Monitoring and Dose Adjustment: Adjust the dose of PROMACTA in 50 mg increments every 2 weeks as necessary to achieve the target platelet count greater than or equal to 50 x 10^9/L as necessary. Do not exceed a dose of 150 mg daily. Monitor clinical hematology and liver tests regularly throughout therapy with PROMACTA and modify the dosage regimen of PROMACTA based on platelet counts as outlined in Table 7.

Table 7. Dose Adjustments of PROMACTA in Patients With Refractory Severe Aplastic Anemia
Platelet count result | Dose adjustment or response
< 50 x 10^9/L following at least 2 weeks of PROMACTA | Increase daily dose by 50 mg to a maximum of 150 mg/day.; For patients taking 25 mg once daily, increase the dose to 50 mg daily before increasing the dose amount by 50 mg.
≥ 200 x 10^9/L to ≤ 400 x 10^9/L at any time | Decrease the daily dose by 50 mg. Wait 2 weeks to assess the effects of this and any subsequent dose adjustments.
> 400 x 10^9/L | Stop PROMACTA for 1 week.; Once the platelet count is < 150 x 10^9/L, reinitiate therapy at a dose reduced by 50 mg.
> 400 x 10^9/L after 2 weeks of therapy at lowest dose of PROMACTA | Discontinue PROMACTA.

For patients who achieve tri-lineage response, including transfusion independence, lasting at least 8 weeks: the dose of PROMACTA may be reduced by 50% [see Clinical Studies (14.3)]. If counts remain stable after 8 weeks at the reduced dose, then discontinue PROMACTA and monitor blood counts. If platelet counts drop to less than 30 x 10^9/L, hemoglobin to less than 9 g/dL, or absolute neutrophil count (ANC) to less than 0.5 x 10^9/L, PROMACTA may be reinitiated at the previous effective dose.

Discontinuation: If no hematologic response has occurred after 16 weeks of therapy with PROMACTA, discontinue therapy. If new cytogenetic abnormalities are observed, consider discontinuation of PROMACTA [see Adverse Reactions (6.1)]. Excessive platelet count responses (as outlined in Table 7) or important liver test abnormalities also necessitate discontinuation of PROMACTA [see Warnings and Precautions (5.2)].

2.4 Administration

Administration of Tablets and Oral Suspension: Take PROMACTA without a meal or with a meal low in calcium (≤ 50 mg). Take PROMACTA at least 2 hours before or 4 hours after other medications (e.g., antacids), calcium-rich foods (containing > 50 mg calcium e.g., dairy products, calcium-fortified juices, and certain fruits and vegetables), or supplements containing polyvalent cations, such as iron, calcium, aluminum, magnesium, selenium, and zinc [see Drug Interactions (7.1), Clinical Pharmacology (12.3)].

Do not split, chew, or crush tablets and mix with food or liquids.

Preparation of the Oral Suspension: Prior to use of the oral suspension, ensure patients or caregivers receive training on proper dosing, preparation, and administration of PROMACTA for oral suspension.

Administer the oral suspension immediately after preparation. Discard any suspension not administered within 30 minutes after preparation.

Prepare the suspension with water only. NOTE: Do not use hot water to prepare the suspension.

For details on preparation and administration of the suspension, including the recommended duration of use of each oral dosing syringe [see Instructions for Use].

3 DOSAGE FORMS AND STRENGTHS

Tablets

- 12.5 mg tablets —– round, biconvex, white, film-coated tablets debossed with “GS MZ1” and 12.5 on one side. Each tablet, for oral administration, contains eltrombopag olamine, equivalent to 12.5 mg of eltrombopag free acid.
- 25 mg tablets —– round, biconvex, orange, film-coated tablets debossed with “GS NX3” and 25 on one side. Each tablet, for oral administration, contains eltrombopag olamine, equivalent to 25 mg of eltrombopag free acid.
- 50 mg tablets —– round, biconvex, blue, film-coated tablets debossed with “GS UFU” and 50 on one side. Each tablet, for oral administration, contains eltrombopag olamine, equivalent to 50 mg of eltrombopag free acid.
- 75 mg tablets —– round, biconvex, pink, film-coated tablets debossed with “GS FFS” and 75 on one side. Each tablet, for oral administration, contains eltrombopag olamine, equivalent to 75 mg of eltrombopag free acid.

For Oral Suspension

- 12.5 mg packet —– contains a reddish-brown to yellow powder for reconstitution.
- 25 mg packet —– contains a reddish-brown to yellow powder for reconstitution.

4 CONTRAINDICATIONS

None.

5 WARNINGS AND PRECAUTIONS

5.1 Hepatic Decompensation in Patients With Chronic Hepatitis C

In patients with chronic hepatitis C, PROMACTA in combination with interferon and ribavirin may increase the risk of hepatic decompensation. In two controlled clinical trials in patients with chronic hepatitis C and thrombocytopenia, ascites and encephalopathy occurred more frequently on the arm receiving treatment with PROMACTA plus antivirals (7%) than the placebo plus antivirals arm (4%). Patients with low albumin levels (less than 3.5 g/dL) or Model for End-Stage Liver Disease (MELD) score greater than or equal to 10 at baseline had a greater risk for hepatic decompensation on the arm receiving treatment with PROMACTA plus antivirals. Discontinue PROMACTA if antiviral therapy is discontinued.

5.2 Hepatotoxicity

PROMACTA may increase the risk of severe and potentially life-threatening hepatotoxicity [see Adverse Reactions (6.1)]. One patient (< 1%) with ITP treated with PROMACTA in clinical trials experienced drug-induced liver injury. Eleven patients (1%) with chronic hepatitis C treated with PROMACTA in clinical trials experienced drug-induced liver injury.

Treatment of ITP, Chronic Hepatitis C-associated Thrombocytopenia, and Refractory Severe Aplastic Anemia

Measure serum ALT, AST, and bilirubin prior to initiation of PROMACTA, every 2 weeks during the dose adjustment phase, and monthly following establishment of a stable dose [see Drug Interactions (7.5)]. PROMACTA inhibits UDP-glucuronosyltransferase (UGT)1A1 and organic anion-transporting polypeptide (OATP)1B1, which may lead to indirect hyperbilirubinemia. If bilirubin is elevated, perform fractionation. Evaluate abnormal serum liver tests with repeat testing within 3 to 5 days. If the abnormalities are confirmed, monitor serum liver tests weekly until resolved or stabilized. Discontinue PROMACTA if ALT levels increase to greater than or equal to 3 x ULN in patients with normal liver function or greater than or equal to 3 x baseline (or greater than 5 x ULN, whichever is the lower) in patients with pre-treatment elevations in transaminases and are:

- progressively increasing, or
- persistent for greater than or equal to 4 weeks, or
- accompanied by increased direct bilirubin, or
- accompanied by clinical symptoms of liver injury or evidence for hepatic decompensation.

If the potential benefit for reinitiating treatment with PROMACTA is considered to outweigh the risk for hepatotoxicity, then consider cautiously reintroducing PROMACTA and measure serum liver tests weekly during the dose adjustment phase. Hepatotoxicity may reoccur if PROMACTA is reinitiated. If liver test abnormalities persist, worsen, or recur, then permanently discontinue PROMACTA.

First-Line Treatment of Severe Aplastic Anemia

Measure ALT, AST, and bilirubin prior to initiation of PROMACTA, every other day while hospitalized for h-ATG therapy, and then every 2 weeks during treatment. During treatment, manage increases in ALT or AST levels as recommended in Table 6.

5.3 Increased Risk of Death and Progression of Myelodysplastic Syndromes to Acute Myeloid Leukemia

A randomized, double-blind, placebo-controlled, multicenter trial in patients with International Prognostic Scoring System (IPSS) intermediate-1, intermediate-2 or high risk MDS with thrombocytopenia, receiving azacitidine in combination with either PROMACTA (n = 179) or placebo (n = 177) was terminated due to lack of efficacy and safety reasons, including increased progression to acute myeloid leukemia (AML). Patients received PROMACTA or placebo at a starting dose of 200 mg once daily, up to a maximum of 300 mg once daily, in combination with azacitidine for at least six cycles. The incidence of death (overall survival) was 32% (57/179) in the PROMACTA arm versus 29% (51/177) in the placebo arm (HR [95% CI] = 1.42 [0.97, 2.08], showing an increased relative risk of death in this trial by 42% in the PROMACTA arm). The incidence of progression to AML was 12% (21/179) in the PROMACTA arm versus 6% (10/177) in the placebo arm (HR [95% CI] = 2.66 [1.31, 5.41], showing an increased relative risk of progression to AML in this trial by 166% in the PROMACTA arm).

5.4 Thrombotic/Thromboembolic Complications

Thrombotic/thromboembolic complications may result from increases in platelet counts with PROMACTA. Reported thrombotic/thromboembolic complications included both venous and arterial events and were observed at low and at normal platelet counts.

Consider the potential for an increased risk of thromboembolism when administering PROMACTA to patients with known risk factors for thromboembolism (e.g., Factor V Leiden, ATIII deficiency, antiphospholipid syndrome, chronic liver disease). To minimize the risk for thrombotic/thromboembolic complications, do not use PROMACTA in an attempt to normalize platelet counts. Follow the dose adjustment guidelines to achieve and maintain target platelet counts [see Dosage and Administration (2.1, 2.2, 2.3)].

In two controlled clinical trials in patients with chronic hepatitis C and thrombocytopenia, 3% (31/955) treated with PROMACTA experienced a thrombotic event compared with 1% (5/484) on placebo. The majority of events were of the portal venous system (1% in patients treated with PROMACTA versus less than 1% for placebo).

In a controlled trial in patients with chronic liver disease and thrombocytopenia not related to ITP undergoing elective invasive procedures (N = 292), the risk of thrombotic events was increased in patients treated with 75 mg of PROMACTA once daily. Seven thrombotic complications (six patients) were reported in the group that received PROMACTA and three thrombotic complications were reported in the placebo group (two patients). All of the thrombotic complications reported in the group that received PROMACTA were portal vein thrombosis (PVT). Symptoms of PVT included abdominal pain, nausea, vomiting, and diarrhea. Five of the six patients in the group that received PROMACTA experienced a thrombotic complication within 30 days of completing treatment with PROMACTA and at a platelet count above 200 x 10^9/L. The risk of portal venous thrombosis was increased in thrombocytopenic patients with chronic liver disease treated with 75 mg of PROMACTA once daily for 2 weeks in preparation for invasive procedures.

5.5 Cataracts

In the three controlled clinical trials in adults with persistent or chronic ITP, cataracts developed or worsened in 15 (7%) patients who received 50 mg of PROMACTA daily and 8 (7%) placebo-group patients. In the extension trial, cataracts developed or worsened in 11% of patients who underwent ocular examination prior to therapy with PROMACTA. In the two controlled clinical trials in patients with chronic hepatitis C and thrombocytopenia, cataracts developed or worsened in 8% of patients treated with PROMACTA and 5% of patients treated with placebo.

Cataracts were observed in toxicology studies of eltrombopag in rodents [see Nonclinical Toxicology (13.2)]. Perform a baseline ocular examination prior to administration of PROMACTA and, during therapy with PROMACTA, regularly monitor patients for signs and symptoms of cataracts.

5.6 Laboratory Test Interference

Eltrombopag (PROMACTA) is highly colored and can cause patient sample discoloration, which can interfere with some clinical laboratory tests. Inaccurate test results that are inconsistent with clinical observations may occur for multiple clinical chemistry tests including bilirubin and creatinine. In addition, other lab tests may be impacted, including but not limited to total protein and albumin, and incorrect test results may be generated if there is eltrombopag in the patient’s specimen. Communicate to the lab conducting the testing if your patient is taking PROMACTA. Re-testing using other methods may also help in determining the validity of the test results [see Drug Interactions (7.5)].

6 ADVERSE REACTIONS

The following clinically significant adverse reactions associated with PROMACTA are described in other sections.

- Hepatic Decompensation in Patients with Chronic Hepatitis C [see Warnings and Precautions (5.1)]
- Hepatotoxicity [see Warnings and Precautions (5.2)]
- Increased Risk of Death and Progression of Myelodysplastic Syndromes to Acute Myeloid Leukemia [see Warnings and Precautions (5.3)]
- Thrombotic/Thromboembolic Complications [see Warnings and Precautions (5.4)]
- Cataracts [see Warnings and Precautions (5.5)]

6.1 Clinical Trials Experience

Because clinical trials are conducted under widely varying conditions, adverse reaction rates observed in the clinical trials of a drug cannot be directly compared with rates in the clinical trials of another drug and may not reflect the rates observed in practice.

Persistent or Chronic Immune Thrombocytopenia

Adults: In clinical trials, hemorrhage was the most common serious adverse reaction and most hemorrhagic reactions followed discontinuation of PROMACTA. Other serious adverse reactions included thrombotic/thromboembolic complications [see Warnings and Precautions (5.4)]. The data described below reflect exposure of PROMACTA to patients with persistent or chronic ITP aged 18 to 85 years, of whom 66% were female, in three placebo-controlled trials and one open-label extension trial [see Clinical Studies (14.1)]. PROMACTA was administered to 330 patients for at least 6 months and 218 patients for at least 1 year.

Table 8 presents the most common adverse drug reactions (experienced by greater than or equal to 3% of patients receiving PROMACTA) from the three placebo-controlled trials, with a higher incidence in PROMACTA versus placebo.

Table 8. Adverse Reactions (≥ 3%) From Three Placebo-controlled Trials in Adults With Persistent or Chronic Immune Thrombocytopenia
Adverse reaction | PROMACTA 50 mg; n = 241; (%) | Placebo; n = 128; (%)
Nausea | 9 | 3
Diarrhea | 9 | 7
Upper respiratory tract infection | 7 | 6
Vomiting | 6 | < 1
Urinary tract infectiona | 5 | 4
Increased ALT | 5 | 3
Myalgia | 5 | 2
Oropharyngeal pain | 4 | 3
Increased AST | 4 | 2
Pharyngitis | 4 | 2
Back pain | 3 | 2
Influenza | 3 | 2
Paresthesia | 3 | 2
Rash | 3 | 2
Abbreviations: ALT, alanine aminotransferase; AST, aspartate aminotransferase.
aIncludes PTs of urinary tract infection, cystitis, urinary tract infection bacterial, and bacteriuria.

In the three controlled clinical persistent or chronic ITP trials, alopecia, musculoskeletal pain, blood alkaline phosphatase increased, and dry mouth were the adverse reactions reported in 2% of patients treated with PROMACTA and in no patients who received placebo.

Among 302 patients with persistent or chronic ITP who received PROMACTA in the single-arm extension trial, the adverse reactions occurred in a pattern similar to that seen in the placebo-controlled trials. Table 9 presents the most common treatment-related adverse reactions (experienced by greater than or equal to 3% of patients receiving PROMACTA) from the extension trial.

Table 9. Treatment-related Adverse Reactions (≥ 3%) From Extension Trial in Adults With Persistent or Chronic Immune Thrombocytopenia
Adverse reaction | PROMACTA 50 mg; n = 302; (%)
Headache | 10
ALT increased | 5
AST increased | 5
Cataract | 5
Fatigue | 5
Blood bilirubin increased | 4
Nausea | 4
Hyperbilirubinemia | 3
Diarrhea | 3
Abbreviations: ALT, alanine aminotransferase; AST, aspartate aminotransferase.

In the three controlled persistent or chronic ITP trials, serum liver test abnormalities (predominantly Grade 2 or less in severity) were reported in 11% and 7% of patients for PROMACTA and placebo, respectively. Four patients (1%) treated with PROMACTA and three patients in the placebo group (2%) discontinued treatment due to hepatobiliary laboratory abnormalities. Seventeen of the patients treated with PROMACTA in the controlled trials with hepatobiliary laboratory abnormalities were re-exposed to PROMACTA in the extension trial. Eight of these patients again experienced liver test abnormalities (less than or equal to Grade 3) resulting in discontinuation of PROMACTA in one patient. In the extension persistent or chronic ITP trial, six additional patients had PROMACTA discontinued due to liver test abnormalities (less than or equal to Grade 3).

In the three controlled persistent or chronic ITP trials, cataracts developed or worsened in 7% of patients treated with PROMACTA and 7% of patients in the placebo group. All patients had documented, preexisting risk factors for cataractogenesis, including corticosteroid use. In the extension trial, cataracts developed or worsened in 11% of patients who underwent ocular examination prior to therapy with PROMACTA. Seventy-two percent of patients had preexisting risk factors, including corticosteroid use.

The safety of PROMACTA was also assessed in all patients treated in 7 adult persistent or chronic ITP clinical trials (N = 763 PROMACTA-treated patients and 179 placebo-treated patients). Thromboembolic events were reported in 6% of PROMACTA-treated patients versus 0% of placebo-treated patients and thrombotic microangiopathy with acute renal failure was reported in < 1% of PROMACTA-treated patients versus 0% of placebo-treated patients.

In a placebo-controlled trial of PROMACTA in patients with chronic liver disease and thrombocytopenia not related to ITP, six patients treated with PROMACTA and one patient in the placebo group developed portal vein thromboses [see Warnings and Precautions (5.4)].

Pediatric Patients: The data described below reflect median exposure to PROMACTA of 91 days for 107 pediatric patients (aged 1 to 17 years) with persistent or chronic ITP, of whom 53% were female, across the randomized phase of two placebo-controlled trials.

Table 10 presents the most common adverse drug reactions (experienced by greater than or equal to 3% of pediatric patients 1 year and older receiving PROMACTA) across the two placebo-controlled trials, with a higher incidence for PROMACTA versus placebo.

Table 10. Adverse Reactions (≥ 3%) With a Higher Incidence for PROMACTA Versus Placebo From Two Placebo-controlled Trials in Pediatric Patients 1 Year and Older With Persistent or Chronic Immune Thrombocytopenia
 | PROMACTA | Placebo
 | n = 107 | n = 50
Adverse reaction | (%) | (%)
Upper respiratory tract infection | 17 | 6
Nasopharyngitis | 12 | 4
Cough | 9 | 0
Diarrhea | 9 | 2
Pyrexia | 9 | 8
Abdominal pain | 8 | 4
Oropharyngeal pain | 8 | 2
Toothache | 6 | 0
ALT increaseda | 6 | 0
Rash | 5 | 2
AST increased | 4 | 0
Rhinorrhea | 4 | 0
Abbreviations: ALT, alanine aminotransferase; AST, aspartate aminotransferase.
aIncludes adverse reactions or laboratory abnormalities > 3 x ULN.

In the two controlled clinical persistent or chronic ITP trials, cataracts developed or worsened in 2 (1%) patients treated with PROMACTA. Both patients had received chronic oral corticosteroids, a risk factor for cataractogenesis.

Chronic Hepatitis C-associated Thrombocytopenia: In the two placebo-controlled trials, 955 patients with chronic hepatitis C-associated thrombocytopenia received PROMACTA. Table 11 presents the most common adverse drug reactions (experienced by greater than or equal to 10% of patients receiving PROMACTA compared with placebo).

Table 11. Adverse Reactions (≥ 10% and Greater Than Placebo) From Two Placebo-controlled Trials in Adults With Chronic Hepatitis C
Adverse reaction | PROMACTA; + Peginterferon/Ribavirin; n = 955; (%) | Placebo; + Peginterferon/Ribavirin; n = 484; (%)
Anemia | 40 | 35
Pyrexia | 30 | 24
Fatigue | 28 | 23
Headache | 21 | 20
Nausea | 19 | 14
Diarrhea | 19 | 11
Decreased appetite | 18 | 14
Influenza-like illness | 18 | 16
Insomniaa | 16 | 15
Asthenia | 16 | 13
Cough | 15 | 12
Pruritus | 15 | 13
Chills | 14 | 9
Myalgia | 12 | 10
Alopecia | 10 | 6
Peripheral edema | 10 | 5
aIncludes PTs of insomnia, initial insomnia, and poor quality sleep.

Rash was reported in 9% and 7% of patients receiving PROMACTA and placebo, respectively.

In the two controlled clinical trials in patients with chronic hepatitis C, hyperbilirubinemia was reported in 8% of patients receiving PROMACTA compared with 3% for placebo. Total bilirubin greater than or equal to 1.5 x ULN was reported in 76% and 50% of patients receiving PROMACTA and placebo, respectively. ALT or AST greater than or equal to 3 x ULN was reported in 34% and 38% of patients for PROMACTA and placebo, respectively.

In the two controlled clinical trials in patients with chronic hepatitis C, cataracts developed or worsened in 8% of patients treated with PROMACTA and 5% of patients treated with placebo.

The safety of PROMACTA was also assessed in all patients treated with PROMACTA in the two controlled trials, including patients who initially received PROMACTA in the pre-antiviral treatment phase of the trial and were later randomized to the placebo arm (N = 1520 PROMACTA-treated patients). Hepatic failure was reported in 0.8% of PROMACTA-treated patients and 0.4% of placebo-treated patients.

Severe Aplastic Anemia

First-Line Treatment of Severe Aplastic Anemia

The safety of PROMACTA was established based upon a single-arm trial of 153 patients with severe aplastic anemia who had not received prior definitive immunosuppressive therapy. In this trial, PROMACTA was administered in combination with horse antithymocyte globulin (h-ATG) and cyclosporine [see Clinical Studies (14.3)]. Among the 153 patients who were dosed in this trial, 92 patients were evaluable for safety of the concurrent use of PROMACTA, h-ATG, and cyclosporine at the recommended dose and schedule.

In this cohort, PROMACTA was administered at up to 150 mg once daily on Day 1 to Month 6 (D1-M6) in combination with h-ATG on Days 1 to 4 and cyclosporine for 6 months, followed by low dose of cyclosporine (maintenance dose) for an additional 18 months for patients who achieved a hematologic response at 6 months. The median duration of exposure to PROMACTA in this cohort was 183 days with 70% of patients exposed for > 24 weeks.

Table 12 presents the most common adverse reactions (experienced by greater than or equal to 5% of patients) associated with PROMACTA in the D1-M6 cohort.

Table 12. Adverse Reactions (≥ 5%) From One Open-label Trial in First-Line Treatment of Patients With Severe Aplastic Anemia
Adverse reaction | PROMACTA n = 92 (%)
ALT increased | 29
AST increased | 17
Blood bilirubin increased | 17
Rash | 8
Skin discoloration, including hyperpigmentation | 5
Abbreviations: ALT, alanine aminotransferase; AST, aspartate aminotransferase.

In the PROMACTA D1-M6 cohort, ALT increased (29%), AST increased (17%), and blood bilirubin increased (17%) were reported more frequently than in patients with refractory severe aplastic anemia (see Table 13).

New or worsening liver function laboratory abnormalities (CTCAE Grade 3 and Grade 4) in the PROMACTA D1-M6 cohort were 15% and 2% for AST, 26% and 4% for ALT, and 12% and 1% for bilirubin, respectively.

In this single-arm open-label clinical trial, ALT or AST > 3 x ULN with total bilirubin > 1.5 x ULN and ALT or AST > 3 x ULN with total bilirubin > 2 x ULN were reported in 44% and 32% of patients, respectively, in the PROMACTA D1-M6 cohort.

Pediatric Patients

A total of 34 pediatric patients (2 patients 2 to 5 years of age, 12 patients 6 to 11 years of age, and 20 patients 12 to 16 years of age) were enrolled in this single-arm trial of which 26 pediatric patients were enrolled in the PROMACTA D1-M6 cohort. In this cohort, the most frequent serious adverse reactions (experienced by ≥ 10% of patients) were upper respiratory tract infection (12% in patients age 2 to 16 years compared to 5% in patients 17 years of age and older, respectively) and rash (12% compared to 2%). The most common adverse reactions (experienced by ≥ 10% of patients) associated with PROMACTA were ALT increased (23% in patients age 2 to 16 years compared to 32% in patients 17 years of age and older, respectively), blood bilirubin increased (12% compared to 20%), AST increased (12% compared to 20%), and rash (12% compared to 6%).

Cytogenetic Abnormalities

In this trial, patients had bone marrow aspirates evaluated for cytogenetic abnormalities. Seven patients in the PROMACTA D1-M6 cohort had a new cytogenetic abnormality reported of which 4 had the loss of chromosome 7; these 4 occurred within 6.1 months. Across all cohorts, clonal cytogenetic evolution occurred in 15 out of 153 (10%) patients. Of the 15 patients who experienced a cytogenetic abnormality: 7 patients had the loss of chromosome 7, 6 of which occurred within 6.1 months; 4 patients had chromosomal aberrations which were of unclear significance; 3 patients had a deletion of chromosome 13; and 1 patient had a follow-up bone marrow assessment at 5 years with features of dysplasia with hypercellularity concerning for potential development of MDS. It is unclear whether these findings occurred due to the underlying disease, the immunosuppressive therapy, and/or treatment with PROMACTA.

Refractory Severe Aplastic Anemia

In the single-arm, open-label trial, 43 patients with refractory severe aplastic anemia received PROMACTA. Eleven patients (26%) were treated for greater than 6 months and 7 patients (16%) were treated for greater than 1 year. The most common adverse reactions (greater than or equal to 20%) were nausea, fatigue, cough, diarrhea, and headache.

Table 13. Adverse Reactions (≥ 10%) From One Open-label Trial in Adults With Refractory Severe Aplastic Anemia
Adverse reaction | PROMACTA; n = 43; (%)
Nausea | 33
Fatigue | 28
Cough | 23
Diarrhea | 21
Headache | 21
Pain in extremity | 19
Pyrexia | 14
Dizziness | 14
Oropharyngeal pain | 14
Abdominal pain | 12
Muscle spasms | 12
Transaminases increased | 12
Arthralgia | 12
Rhinorrhea | 12

Rash and hyperbilirubinemia were reported in 7% of patients; cataract was reported in 2% of patients.

In this trial, concurrent ALT or AST greater than 3 x ULN with total bilirubin greater than 1.5 x ULN were reported in 5% of patients. Total bilirubin greater than 1.5 x ULN occurred in 14% of patients.

In this trial, patients had bone marrow aspirates evaluated for cytogenetic abnormalities. Eight patients had a new cytogenetic abnormality reported on therapy, including 5 patients who had complex changes in chromosome 7.

6.2 Postmarketing Experience

The following adverse reactions have been identified during post approval use of PROMACTA. Because these reactions are reported voluntarily from a population of uncertain size, it is not always possible to reliably estimate the frequency or establish a causal relationship to drug exposure.

Skin and Subcutaneous Tissue Disorders: Skin discoloration, including hyperpigmentation and skin yellowing.

7 DRUG INTERACTIONS

7.1 Polyvalent Cations (Chelation)

Eltrombopag chelates polyvalent cations (such as iron, calcium, aluminum, magnesium, selenium, and zinc) in foods, mineral supplements, and antacids.

Take PROMACTA at least 2 hours before or 4 hours after any medications or products containing polyvalent cations, such as antacids, dairy products, and mineral supplements to avoid significant reduction in absorption of PROMACTA due to chelation [see Dosage and Administration (2.4), Clinical Pharmacology (12.3)].

7.2 Transporters

Use caution when concomitantly administering PROMACTA and drugs that are substrates of OATP1B1 (e.g., atorvastatin, bosentan, ezetimibe, fluvastatin, glyburide, olmesartan, pitavastatin, pravastatin, rosuvastatin, repaglinide, rifampin, simvastatin acid, SN-38 [active metabolite of irinotecan], valsartan) or breast cancer resistance protein (BCRP) (e.g., imatinib, irinotecan, lapatinib, methotrexate, mitoxantrone, rosuvastatin, sulfasalazine, topotecan). Monitor patients closely for signs and symptoms of excessive exposure to the drugs that are substrates of OATP1B1 or BCRP and consider reduction of the dose of these drugs, if appropriate. In clinical trials with PROMACTA, a dose reduction of rosuvastatin by 50% was recommended.

7.3 Protease Inhibitors

HIV Protease Inhibitors: No dose adjustment is recommended when PROMACTA is coadministered with lopinavir/ritonavir (LPV/RTV). Drug interactions with other HIV protease inhibitors have not been evaluated.

Hepatitis C Virus Protease Inhibitors: No dose adjustments are recommended when PROMACTA is coadministered with boceprevir or telaprevir. Drug interactions with other hepatitis C virus (HCV) protease inhibitors have not been evaluated.

7.4 Peginterferon Alfa-2a/b Therapy

No dose adjustments are recommended when PROMACTA is coadministered with peginterferon alfa-2a (PEGASYS®) or -2b (PEGINTRON®).

7.5 Interference with Clinical Laboratory Tests

Eltrombopag (PROMACTA) is highly colored and can cause patient sample discoloration, which is reported to interfere with some clinical laboratory tests, including, but not limited to bilirubin and creatinine.

Bilirubin Testing: Eltrombopag can cause both positive and negative interference with bilirubin assays. If the laboratory results for bilirubin are inconsistent with clinical observations, further evaluation of liver function should be performed to clarify the clinical status of the patient. Evaluating contemporaneous aminotransferase values (AST, ALT) may help determine the validity of normal total bilirubin levels in the presence of clinical jaundice.

Creatinine Testing: Eltrombopag can cause positive interference with creatinine measurements, leading to falsely elevated creatinine levels. In the event of an unexpected serum creatinine test result, further evaluation of renal function should be performed. Blood urea should be evaluated if serum creatinine is unexpectedly high.

Communicate to the lab conducting testing if the patient is taking PROMACTA. Re-testing using other methods may also help in determining the validity of the test results.

8 USE IN SPECIFIC POPULATIONS

8.1 Pregnancy

Risk Summary

Available data from a small number of published case reports and postmarketing experience with PROMACTA use in pregnant women are insufficient to assess any drug-associated risks for major birth defects, miscarriage, or adverse maternal or fetal outcomes. In animal reproduction and developmental toxicity studies, oral administration of eltrombopag to pregnant rats during organogenesis resulted in embryolethality and reduced fetal weights at maternally toxic doses. These effects were observed at doses resulting in exposures that were six times the human clinical exposure based on area under the curve (AUC) in patients with persistent or chronic ITP at 75 mg/day, and three times the AUC in patients with chronic hepatitis C at 100 mg/day (see Data).

The estimated background risk of major birth defects and miscarriage for the indicated population is unknown. All pregnancies have a background risk of birth defect, loss, or other adverse outcomes. In the U.S. general population, the estimated background risk of major birth defects and of miscarriage in clinically recognized pregnancies is 2% to 4% and 15% to 20%, respectively.

Data

Animal Data

In an early embryonic development study, female rats received oral eltrombopag at doses of 10, 20, or 60 mg/kg/day (0.8, 2, and 6 times, respectively, the human clinical exposure based on AUC in patients with ITP at 75 mg/day and 0.3, 1, and 3 times, respectively, the human clinical exposure based on AUC in patients with chronic hepatitis C at 100 mg/day). Increased pre- and post-implantation loss and reduced fetal weight were observed at the highest dose which also caused maternal toxicity.

In an embryo-fetal development study eltrombopag was administered orally to pregnant rats during the period of organogenesis at doses of 10, 20, or 60 mg/kg/day (0.8, 2, and 6 times, respectively, the human clinical exposure based on AUC in patients with ITP at 75 mg/day and 0.3, 1, and 3 times, respectively, the human clinical exposure based on AUC in patients with chronic hepatitis C at 100 mg/day). Decreased fetal weights (6% to 7%) and a slight increase in the presence of cervical ribs were observed at the highest dose which also caused maternal toxicity. However, no evidence of major structural malformations was observed.

In an embryo-fetal development study eltrombopag was administered orally to pregnant rabbits during the period of organogenesis at doses of 30, 80, or 150 mg/kg/day (0.04, 0.3, and 0.5 times, respectively, the human clinical exposure based on AUC in patients with ITP at 75 mg/day and 0.02, 0.1, and 0.3 times, respectively, the human clinical exposure based on AUC in patients with chronic hepatitis C at 100 mg/day). No evidence of fetotoxicity, embryolethality, or teratogenicity was observed.

In a pre- and post-natal developmental toxicity study in pregnant rats (F0), oral eltrombopag was administered from gestation Day 6 through lactation Day 20. No adverse effects on maternal reproductive function or on the development of the offspring (F1) were observed at doses up to 20 mg/kg/day (2 times the human clinical exposure based on AUC in patients with ITP at 75 mg/day and similar to the human clinical exposure based on AUC in patients with chronic hepatitis C at 100 mg/day). Eltrombopag was detected in the plasma of offspring (F1). The plasma concentrations in pups increased with dose following administration of drug to the F0 dams.

8.2 Lactation

Risk Summary

There are no data regarding the presence of eltrombopag or its metabolites in human milk, the effects on the breastfed child, or the effects on milk production. However, eltrombopag was detected in the pups of lactating rats 10 days postpartum suggesting the potential for transfer during lactation. Due to the potential for serious adverse reactions in a breastfed child from PROMACTA, breastfeeding is not recommended during treatment.

8.3 Females and Males of Reproductive Potential

Contraception

Based on animal reproduction studies, PROMACTA can cause fetal harm when administered to a pregnant woman. Sexually-active females of reproductive potential should use effective contraception (methods that result in less than 1% pregnancy rates) when using PROMACTA during treatment and for at least 7 days after stopping treatment with PROMACTA.

8.4 Pediatric Use

The safety and efficacy of PROMACTA have been established in pediatric patients 1 year and older with persistent or chronic ITP and in pediatric patients 2 years and older with IST-naïve severe aplastic anemia (in combination with h-ATG and cyclosporine). Safety and efficacy in pediatric patients below the age of 1 year with ITP have not been established. Safety and efficacy in pediatric patients with thrombocytopenia associated with chronic hepatitis C and refractory severe aplastic anemia have not been established.

The safety and efficacy of PROMACTA in pediatric patients 1 year and older with persistent or chronic ITP were evaluated in two double-blind, placebo-controlled trials [see Adverse Reactions (6.1), Clinical Studies (14.1)]. The pharmacokinetics of eltrombopag have been evaluated in 168 pediatric patients 1 year and older with ITP dosed once daily [see Clinical Pharmacology (12.3)]. See Dosage and Administration (2.1) for dosing recommendations for pediatric patients 1 year and older.

The safety and efficacy of PROMACTA in combination with h-ATG and cyclosporine for the first-line treatment of severe aplastic anemia in pediatric patients 2 years and older were evaluated in a single-arm, open-label trial [see Adverse Reactions (6.1), Clinical Studies (14.3)]. A total of 26 pediatric patients (ages 2 to < 17 years) were evaluated; 12 children (aged 2 to < 12 years) and 14 adolescents (aged 12 to < 17). See Dosage and Administration (2.3) for dosing recommendations for pediatric patients 2 years and older. The safety and efficacy of PROMACTA in combination with h-ATG and cyclosporine in pediatric patients younger than 2 years for the first-line treatment of severe aplastic anemia have not yet been established. In patients 2 to 16 years of age, 69% of patients experienced serious adverse events compared to 42% in patients 17 years and older. Among the 12 patients who were 2 to 11 years of age in the PROMACTA D1-M6 cohort and reached the 6-month assessment or withdrew earlier, the complete response rate at Month 6 was 8% versus 46% in patients age 12 to 16 years and 50% in patients 17 years of age and older.

8.5 Geriatric Use

Of the 106 patients in two randomized clinical trials of PROMACTA 50 mg in persistent or chronic ITP, 22% were 65 years of age and over, while 9% were 75 years of age and over. Of the 1439 patients in two randomized clinical trials of PROMACTA in patients with chronic hepatitis C and thrombocytopenia, 7% were 65 years of age and over, while < 1% were 75 years of age and over. Of the 196 patients who received PROMACTA for the treatment of severe aplastic anemia, 18% were 65 years of age and over, while 3% were 75 years of age and over. No overall differences in safety or effectiveness were observed between these patients and younger patients.

8.6 Hepatic Impairment

Patients With Persistent or Chronic ITP and Severe Aplastic Anemia

Reduce the initial dose of PROMACTA in patients with persistent or chronic ITP (adult and pediatric patients 6 years and older only) or refractory severe aplastic anemia who also have hepatic impairment (Child-Pugh class A, B, C) [see Dosage and Administration (2.1, 2.3), Warnings and Precautions (5.2), Clinical Pharmacology (12.3)].

In a clinical trial in patients with severe aplastic anemia who had not received prior definitive immunosuppressive therapy, patients with baseline ALT or AST > 5 x ULN were ineligible to participate. If a patient with hepatic impairment (Child-Pugh class A, B, C) initiates therapy with PROMACTA for the first-line treatment of severe aplastic anemia, reduce the initial dose [see Dosage and Administration (2.3), Warnings and Precautions (5.2), Clinical Pharmacology (12.3)].

Patients With Chronic Hepatitis C

No dosage adjustment is recommended in patients with chronic hepatitis C and hepatic impairment [see Clinical Pharmacology (12.3)].

8.7 Ethnicity

Reduce the initial dose of PROMACTA for patients of East-/Southeast-Asian ancestry with ITP (adult and pediatric patients 6 years and older only) or severe aplastic anemia [see Dosage and Administration (2.1, 2.3), Clinical Pharmacology (12.3)]. No reduction in the initial dose of PROMACTA is recommended in patients of East-/Southeast-Asian ancestry with chronic hepatitis C [see Clinical Pharmacology (12.3)].

10 OVERDOSAGE

In the event of overdose, platelet counts may increase excessively and result in thrombotic/thromboembolic complications.

In one report, a subject who ingested 5000 mg of PROMACTA had a platelet count increase to a maximum of 929 x 10^9/L at 13 days following the ingestion. The patient also experienced rash, bradycardia, ALT/AST elevations, and fatigue. The patient was treated with gastric lavage, oral lactulose, intravenous fluids, omeprazole, atropine, furosemide, calcium, dexamethasone, and plasmapheresis; however, the abnormal platelet count and liver test abnormalities persisted for 3 weeks. After 2 months’ follow-up, all events had resolved without sequelae.

In case of an overdose, consider oral administration of a metal cation-containing preparation, such as calcium, aluminum, or magnesium preparations to chelate eltrombopag and thus limit absorption. Closely monitor platelet counts. Reinitiate treatment with PROMACTA in accordance with dosing and administration recommendations [see Dosage and Administration (2.1, 2.2)]. Consider contacting the Poison Help line (1-800-222-1222) or a medical toxicologist for additional overdose management recommendations.

11 DESCRIPTION

PROMACTA (eltrombopag) tablets contain eltrombopag olamine, a small molecule thrombopoietin (TPO) receptor agonist for oral administration.

Eltrombopag olamine is a biphenyl hydrazone. The chemical name for eltrombopag olamine is 3'-{(2Z)-2-[1-(3,4-dimethylphenyl)-3-methyl-5-oxo-1,5-dihydro-4H-pyrazol-4-ylidene]hydrazino}-2'-hydroxy-3-biphenylcarboxylic acid - 2-aminoethanol (1:2). It has the molecular formula C25H22N4O4 • 2(C2H7NO). The molecular weight is 564.65 g/mol for eltrombopag olamine and 442.5 g/mol for eltrombopag free acid. Eltrombopag olamine has the following structural formula:

Eltrombopag olamine is practically insoluble in aqueous buffer across a pH range of 1 to 7.4, and is sparingly soluble in water.

PROMACTA (eltrombopag) tablets contain eltrombopag olamine in the amount equivalent to 12.5 mg, 25 mg, 50 mg, or 75 mg of eltrombopag free acid. The inactive ingredients of PROMACTA tablets are:

Tablet Core: magnesium stearate, mannitol, microcrystalline cellulose, povidone, and sodium starch glycolate.
Coating: FD&C Blue No. 2 aluminum lake (50-mg tablet), FD&C Yellow No. 6 aluminum lake (25-mg tablet), hypromellose, Iron Oxide Black and Iron Oxide Red (75-mg tablet), polyethylene glycol 400, polysorbate 80 (12.5-mg tablet), or titanium dioxide.

PROMACTA (eltrombopag) for oral suspension packets contain a reddish-brown to yellow powder which produces a reddish-brown suspension when reconstituted with water. Each packet delivers eltrombopag olamine equivalent to 12.5 mg or 25 mg of eltrombopag free acid. The inactive ingredients of PROMACTA for oral suspension are mannitol, sucralose, and xanthan gum.

12 CLINICAL PHARMACOLOGY

12.1 Mechanism of Action

Eltrombopag is a TPO-receptor agonist that interacts with the transmembrane domain of the human TPO-receptor (also known as cMpl) and initiates signaling cascades that induce proliferation and differentiation of megakaryocytes leading to increased platelet production.

12.2 Pharmacodynamics

In clinical trials, treatment with PROMACTA resulted in dose-dependent increases in platelet counts following repeated (daily) dosing. The increase in platelet counts reached a maximum approximately two weeks after the initiation of dosing, and returned to baseline within approximately two weeks after the last dose of PROMACTA.

Cardiac Electrophysiology

At doses up to 150 mg (the maximum recommended dose) daily for 5 days, PROMACTA did not prolong the QT/QTc interval to any relevant extent.

12.3 Pharmacokinetics

Eltrombopag demonstrated a dose-proportional increase in exposure between doses of 50 to 150 mg/day in healthy adult subjects. Eltrombopag AUC was approximately 1.7-fold higher in patients with persistent or chronic ITP and approximately 2.8-fold higher in patients with HCV compared to healthy subjects. Steady-state was achieved after approximately 1 week of once daily treatment, with geometric mean accumulation ratio of 1.56 (90% confidence interval 1.20, 1.63) at 75 mg/day. Eltrombopag AUC was approximately 3.2-fold higher in patients with definitive immunosuppressive therapy-naïve severe aplastic anemia compared to healthy subjects suggesting higher relative exposure compared to healthy subjects or patients with ITP and similar exposure compared to patients with chronic hepatitis C. Eltrombopag for oral suspension delivered 22% higher plasma AUC0-INF than the tablet formulation.

Absorption

Eltrombopag is absorbed with a peak concentration occurring 2 to 6 hours after oral administration. Oral absorption of drug-related material following administration of a single 75-mg solution dose was estimated to be at least 52%.

Effect of Food

A standard high-fat breakfast (876 calories, 52 g fat, 71 g carbohydrate, 34 g protein, and 427 mg calcium) significantly decreased plasma eltrombopag AUC0-INF by approximately 59% and Cmax by 65% and delayed Tmax by 1 hour. The decrease in exposure is primarily due to the high calcium content.

A meal low in calcium (≤ 50 mg calcium) did not significantly impact plasma eltrombopag exposure, regardless of calorie and fat content.

The effect of administration of a single 25-mg dose of eltrombopag for oral suspension with a high-calcium, moderate-fat, moderate calorie meal on AUC0-INF and Cmax in healthy adult subjects is presented in Table 14.

Table 14. Effect on Plasma Eltrombopag Pharmacokinetic Parameters After Administration of a Single 25-mg Dose of Eltrombopag for Oral Suspension With a High Calcium Meala in Healthy Adult Subjects
Timing of eltrombopag for oral suspension dose | Mean (90% CI) reduction in plasma eltrombopag AUC0-INF | Mean (90% CI) reduction in plasma eltrombopag Cmax
With a high-calcium, moderate-fat, moderate-calorie meal | 75% (71%, 88%) | 79% (76%, 82%)
2 hours after the high-calcium, moderate-fat, moderate-calorie meal | 47% (40%, 53%) | 48% (40%, 54%)
2 hours before the high-calcium, moderate-fat, moderate-calorie meal | 20% (9%, 29%) | 14% (2%, 25%)
a372 calories, 9 g fat, and 448 mg calcium.

Distribution

The concentration of eltrombopag in blood cells is approximately 50% to 79% of plasma concentrations based on a radiolabel study. In vitro studies suggest that eltrombopag is highly bound to human plasma proteins (greater than 99%). Eltrombopag is a substrate of BCRP, but is not a substrate for P-glycoprotein (P-gp) or OATP1B1.

Elimination

The plasma elimination half-life of eltrombopag is approximately 21 to 32 hours in healthy subjects and 26 to 35 hours in patients with ITP.

Metabolism: Absorbed eltrombopag is extensively metabolized, predominantly through pathways, including cleavage, oxidation, and conjugation with glucuronic acid, glutathione, or cysteine. In vitro studies suggest that CYP1A2 and CYP2C8 are responsible for the oxidative metabolism of eltrombopag. UGT1A1 and UGT1A3 are responsible for the glucuronidation of eltrombopag.

Excretion: The predominant route of eltrombopag excretion is via feces (59%), and 31% of the dose is found in the urine. Unchanged eltrombopag in feces accounts for approximately 20% of the dose; unchanged eltrombopag is not detectable in urine.

Specific Populations

Ethnicity

Eltrombopag concentrations in East-/Southeast-Asian ancestry patients with ITP or chronic hepatitis C were 50% to 55% higher compared with non-Asian subjects [see Dosage and Administration (2.1, 2.3)].

Eltrombopag exposure in healthy African-American subjects was approximately 40% higher than that observed in Caucasian subjects in one clinical pharmacology trial and similar in three other clinical pharmacology trials. The effect of African-American ethnicity on exposure and related safety and efficacy of eltrombopag has not been established.

Hepatic Impairment

Following a single dose of PROMACTA (50 mg), plasma eltrombopag AUC0-INF was 41% higher in patients with mild hepatic impairment (Child-Pugh class A) compared with subjects with normal hepatic function. Plasma eltrombopag AUC0-INF was approximately 2-fold higher in patients with moderate (Child-Pugh class B) and severe hepatic impairment (Child-Pugh class C) compared with subjects with normal hepatic function. The half-life of eltrombopag was prolonged 2-fold in these patients. This clinical trial did not evaluate protein-binding effects.

Chronic Liver Disease

Following repeat doses of eltrombopag in patients with thrombocytopenia and with chronic liver disease, mild hepatic impairment resulted in an 87% to 110% higher plasma eltrombopag AUC(0-τ) and moderate hepatic impairment resulted in approximately 141% to 240% higher plasma eltrombopag AUC(0-τ) values compared with patients with normal hepatic function. The half-life of eltrombopag was prolonged 3-fold in patients with mild hepatic impairment and 4-fold in patients with moderate hepatic impairment. This clinical trial did not evaluate protein-binding effects.

Chronic Hepatitis C

Patients with chronic hepatitis C treated with PROMACTA had higher plasma AUC(0-τ) values as compared with healthy subjects, and AUC(0-τ) increased with increasing Child-Pugh score. Patients with chronic hepatitis C and mild hepatic impairment had approximately 100% to 144% higher plasma AUC(0-τ) compared with healthy subjects. This clinical trial did not evaluate protein-binding effects.

Renal Impairment

Following a single dose of PROMACTA (50 mg), the average total plasma eltrombopag AUC0-INF was 32% to 36% lower in subjects with mild (estimated creatinine clearance (CLCr) by Cockcroft-Gault equation: 50 to 80 mL/min), to moderate (CLCr of 30 to 49 mL/min) renal impairment and 60% lower in subjects with severe (CLCr less than 30 mL/min) renal impairment compared with healthy subjects. The effect of renal impairment on unbound (active) eltrombopag exposure has not been assessed.

Pediatric Patients

The pharmacokinetics of eltrombopag have been evaluated in 168 pediatric patients 1 year and older with ITP dosed once daily in two trials. Plasma eltrombopag apparent clearance following oral administration (CL/F) increased with increasing body weight. East-/Southeast-Asian pediatric patients with ITP had approximately 43% higher plasma eltrombopag AUC(0-τ) values as compared with non-Asian patients.

Plasma eltrombopag AUC(0-τ) and Cmax in pediatric patients aged 12 to 17 years was similar to that observed in adults. The pharmacokinetic parameters of eltrombopag in pediatric patients with ITP are shown in Table 15.

Table 15. Geometric Mean (95% CI) Steady-state Plasma Eltrombopag Pharmacokinetic Parametersa in Patients With ITP (Normalized to a Once-daily 50-mg Dose)
 | Cmaxb | AUC(0-τ)b
Age | (mcg/mL) | (mcg·hr/mL)
Adults (n = 108) | 7.03 | 101
 | (6.44, 7.68) | (91.4, 113)
12 to 17 years (n = 62) | 6.80 | 103
 | (6.17, 7.50) | (91.1, 116)
6 to 11 years (n = 68) | 10.3 | 153
 | (9.42, 11.2) | (137, 170)
1 to 5 years (n = 38) | 11.6 | 162
 | (10.4, 12.9) | (139, 187)
aPK parameters presented as geometric mean (95% CI).
bBased on population PK post-hoc estimates.

Drug Interaction Studies

Clinical Studies

Effect of Drugs on Eltrombopag

Effect of Polyvalent Cation-containing Antacids on Eltrombopag:

The coadministration of a single dose of PROMACTA (75 mg) with a polyvalent cation-containing antacid (1,524 mg aluminum hydroxide, 1,425 mg magnesium carbonate, and sodium alginate) decreased plasma eltrombopag AUC0-INF and Cmax by approximately 70%. The contribution of sodium alginate to this interaction is not known.

Effect of HIV Protease Inhibitors on Eltrombopag:

The coadministration of repeat-dose lopinavir 400 mg/ritonavir 100 mg (twice daily) with a single dose of PROMACTA (100 mg) decreased plasma eltrombopag AUC0-INF by 17%.

Effect of HCV Protease Inhibitors on Eltrombopag:

The coadministration of repeat-dose telaprevir (750 mg every 8 hours) or boceprevir (800 mg every 8 hours) with a single dose of PROMACTA (200 mg) to healthy adult subjects in a clinical trial did not alter plasma eltrombopag AUC0-INF or Cmax to a significant extent.

Effect of Cyclosporine on Eltrombopag:

The coadministration of a single dose of PROMACTA (50 mg) with a single dose of an OATP and BCRP inhibitor cyclosporine (200 mg or 600 mg) decreased plasma eltrombopag AUC0-INF by 18% to 24% and Cmax by 25% to 39%.

Effect of Pegylated Interferon alfa-2a + Ribavirin and Pegylated Interferon alfa-2b + Ribavirin on Eltrombopag:

The presence of pegylated interferon alfa + ribavirin therapy did not significantly affect the clearance of eltrombopag.

Effect of Eltrombopag on Other Drugs

Effect of Eltrombopag on Cytochrome P450 Enzymes Substrates:

The coadministration of multiple doses of PROMACTA (75 mg once daily for 7 days) did not result in the inhibition or induction of the metabolism of a combination of probe substrates for CYP1A2 (caffeine), CYP2C19 (omeprazole), CYP2C9 (flurbiprofen), or CYP3A4 (midazolam) in humans.

Effect of Eltrombopag on Rosuvastatin:

The coadministration of multiple doses of PROMACTA (75 mg once daily for 5 days) with a single dose of rosuvastatin (OATP1B1 and BCRP substrate; 10 mg) increased plasma rosuvastatin AUC0-INF by 55% and Cmax by 103%.

Effect of Eltrombopag on HCV Protease Inhibitors:

The coadministration of repeat-dose telaprevir (750 mg every 8 hours) or boceprevir (800 mg every 8 hours) with a single dose of PROMACTA (200 mg) to healthy adult subjects in a clinical trial did not alter plasma telaprevir or boceprevir AUC0-INF or Cmax to a significant extent.

In vitro Studies

Eltrombopag Effect on Metabolic Enzymes

Eltrombopag has demonstrated the potential to inhibit CYP2C8, CYP2C9, UGT1A1, UGT1A3, UGT1A4, UGT1A6, UGT1A9, UGT2B7, and UGT2B15.

Eltrombopag Effect on Transporters

Eltrombopag has demonstrated the potential to inhibit OATP1B1 and BCRP.

13 NONCLINICAL TOXICOLOGY

13.1 Carcinogenesis, Mutagenesis, Impairment of Fertility

Eltrombopag does not stimulate platelet production in rats, mice, or dogs because of unique TPO receptor specificity. Data from these animals do not fully model effects in humans.

Eltrombopag was not carcinogenic in mice at doses up to 75 mg/kg/day or in rats at doses up to 40 mg/kg/day (exposures up to 4 times the human clinical exposure based on AUC in patients with ITP at 75 mg/day and 2 times the human clinical exposure based on AUC in patients with chronic hepatitis C at 100 mg/day).

Eltrombopag was not mutagenic or clastogenic in a bacterial mutation assay or in two in vivo assays in rats (micronucleus and unscheduled DNA synthesis, 10 times the human clinical exposure based on Cmax in patients with ITP at 75 mg/day and 7 times the human clinical exposure based on Cmax in patients with chronic hepatitis C at 100 mg/day). In the in vitro mouse lymphoma assay, eltrombopag was marginally positive (less than 3-fold increase in mutation frequency).

Eltrombopag did not affect female fertility in rats at doses up to 20 mg/kg/day (2 times the human clinical exposure based on AUC in patients with ITP at 75 mg/day and similar to the human clinical exposure based on AUC in patients with chronic hepatitis C at 100 mg/day). Eltrombopag did not affect male fertility in rats at doses up to 40 mg/kg/day, the highest dose tested (3 times the human clinical exposure based on AUC in patients with ITP at 75 mg/day and 2 times the human clinical exposure based on AUC in patients with chronic hepatitis C at 100 mg/day).

13.2 Animal Pharmacology and/or Toxicology

Treatment-related cataracts were detected in rodents in a dose- and time-dependent manner. At greater than or equal to 6 times the human clinical exposure based on AUC in patients with ITP at 75 mg/day and 3 times the human clinical exposure based on AUC in patients with chronic hepatitis C at 100 mg/day, cataracts were observed in mice after 6 weeks and in rats after 28 weeks of dosing. At greater than or equal to 4 times the human clinical exposure based on AUC in patients with ITP at 75 mg/day and 2 times the human clinical exposure based on AUC in patients with chronic hepatitis C at 100 mg/day, cataracts were observed in mice after 13 weeks and in rats after 39 weeks of dosing [see Warnings and Precautions (5.5)].

Renal tubular toxicity was observed in studies up to 14 days in duration in mice and rats at exposures that were generally associated with morbidity and mortality. Tubular toxicity was also observed in a 2-year oral carcinogenicity study in mice at doses of 25, 75, and 150 mg/kg/day. The exposure at the lowest dose was 1.2 times the human clinical exposure based on AUC in patients with ITP at 75 mg/day and 0.6 times the human clinical exposure based on AUC in patients with chronic hepatitis C at 100 mg/day. No similar effects were observed in mice after 13 weeks at exposures greater than those associated with renal changes in the 2-year study, suggesting that this effect is both dose- and time-dependent.

14 CLINICAL STUDIES

14.1 Persistent or Chronic ITP

Adults: The efficacy and safety of PROMACTA in adult patients with persistent or chronic ITP were evaluated in three randomized, double-blind, placebo-controlled trials and in an open-label extension trial.

In Study TRA100773B and Study TRA100773A (referred to as Study 773B and Study 773A, respectively [NCT00102739]), patients who had completed at least one prior ITP therapy and who had a platelet count less than 30 x 10^9/L were randomized to receive either PROMACTA or placebo daily for up to 6 weeks, followed by 6 weeks off therapy. During the trials, PROMACTA or placebo was discontinued if the platelet count exceeded 200 x 10^9/L.

The median age of the patients was 50 years and 60% were female. Approximately 70% of the patients had received at least 2 prior ITP therapies (predominantly corticosteroids, immunoglobulins, rituximab, cytotoxic therapies, danazol, and azathioprine) and 40% of the patients had undergone splenectomy. The median baseline platelet counts (approximately 18 x 10^9/L) were similar among all treatment groups.

Study 773B randomized 114 patients (2:1) to PROMACTA 50 mg or placebo. Of 60 patients with documented time since diagnosis, approximately 17% met the definition of persistent ITP with time since diagnosis of 3-12 months. Study 773A randomized 117 patients (1:1:1:1) among placebo or 1 of 3 dose regimens of PROMACTA, 30 mg, 50 mg, or 75 mg each administered daily. Of 51 patients with documented time since diagnosis, approximately 14% met the definition of persistent ITP.

The efficacy of PROMACTA in this trial was evaluated by response rate, defined as a shift from a baseline platelet count of less than 30 x 10^9/L to greater than or equal to 50 x 10^9/L at any time during the treatment period (Table 16).

Table 16. Studies 773B and 773A: Platelet Count Response (≥ 50 x 10^9/L) Rates in Adults With Persistent or Chronic Immune Thrombocytopenia
Study | PROMACTA; 50 mg Daily | Placebo
773B | 43/73 (59%)a | 6/37 (16%)
773A | 19/27 (70%)a | 3/27 (11%)
a p-value < 0.001 for PROMACTA versus placebo.

The platelet count response to PROMACTA was similar among patients who had or had not undergone splenectomy. In general, increases in platelet counts were detected 1 week following initiation of PROMACTA and the maximum response was observed after 2 weeks of therapy. In the placebo and 50-mg–dose groups of PROMACTA, the trial drug was discontinued due to an increase in platelet counts to greater than 200 x 10^9/L in 3% and 27% of the patients, respectively. The median duration of treatment with the 50-mg dose of PROMACTA was 43 days in Study 773B and 42 days in Study 773A.

Of 7 patients who underwent hemostatic challenges, additional ITP medications were required in 3 of 3 placebo group patients and 0 of 4 patients treated with PROMACTA. Surgical procedures accounted for most of the hemostatic challenges. Hemorrhage requiring transfusion occurred in one placebo group patient and no patients treated with PROMACTA.

In the RAISE study (NCT00370331), 197 patients were randomized (2:1) to receive either PROMACTA 50 mg once daily (n = 135) or placebo (n = 62) for 6 months, during which time the dose of PROMACTA could be adjusted based on individual platelet counts. Of 145 patients with documented time since diagnosis, 19% met the definition of persistent ITP. Patients were allowed to taper or discontinue concomitant ITP medications after being treated with PROMACTA for 6 weeks. Patients were permitted to receive rescue treatments at any time during the trial as clinically indicated.

The median ages of the patients treated with PROMACTA and placebo were 47 years and 52.5 years, respectively. Approximately half of the patients treated with PROMACTA and placebo (47% and 50%, respectively) were receiving concomitant ITP medication (predominantly corticosteroids) at randomization and had baseline platelet counts less than or equal to 15 x 10^9/L (50% and 48%, respectively). A similar percentage of patients treated with PROMACTA and placebo (37% and 34%, respectively) had a prior splenectomy.

The efficacy of PROMACTA in this trial was evaluated by the odds of achieving a platelet count greater than or equal to 50 x 10^9/L and less than or equal to 400 x 10^9/L for patients receiving PROMACTA relative to placebo and was based on patient response profiles throughout the 6-month treatment period. In 134 patients who completed 26 weeks of treatment, a sustained platelet response (platelet count greater than or equal to 50 x 10^9/L and less than or equal to 400 x 10^9/L for 6 out of the last 8 weeks of the 26-week treatment period in the absence of rescue medication at any time) was achieved by 60% of patients treated with PROMACTA, compared with 10% of patients treated with placebo (splenectomized patients: PROMACTA 51%, placebo 8%; non-splenectomized patients: PROMACTA 66%, placebo 11%). The proportion of responders in the group of patients treated with PROMACTA was between 37% and 56% compared with 7% and 19% in the placebo treatment group for all on-therapy visits. Patients treated with PROMACTA were significantly more likely to achieve a platelet count between 50 x 10^9/L and 400 x 10^9/L during the entire 6-month treatment period compared with those patients treated with placebo.

Outcomes of treatment are presented in Table 17 for all patients enrolled in the trial.

Table 17. RAISE: Outcomes of Treatment in Adults With Persistent or Chronic Immune Thrombocytopenia
Outcome | PROMACTA; n = 135 | Placebo; n = 62
Mean number of weeks with platelet counts ≥ 50 x 10^9/L | 11.3 | 2.4
Requiring rescue therapy, n (%) | 24 (18) | 25 (40)

Among 94 patients receiving other ITP therapy at baseline, 37 (59%) of 63 patients treated with PROMACTA and 10 (32%) of 31 patients in the placebo group discontinued concomitant therapy at some time during the trial.

In the EXTEND study (NCT00351468), patients who completed any prior clinical trial with PROMACTA were enrolled in an open-label, single-arm trial in which attempts were made to decrease the dose or eliminate the need for any concomitant ITP medications. PROMACTA was administered to 302 patients in EXTEND; 218 patients completed 1 year, 180 patients completed 2 years, 107 patients completed 3 years, 75 patients completed 4 years, 34 patients completed 5 years, and 18 patients completed 6 years of therapy. The median baseline platelet count was 19 x 10^9/L prior to administration of PROMACTA. Median platelet counts at 1, 2, 3, 4, 5, 6, and 7 years on study were 85 x 10^9/L, 85 x 10^9/L, 105 x 10^9/L, 64 x 10^9/L, 75 x 10^9/L, 119 x 10^9/L, and 76 x 10^9/L, respectively.

Pediatric Patients: The efficacy and safety of PROMACTA in pediatric patients 1 year and older with persistent or chronic ITP were evaluated in two double-blind, placebo-controlled trials. The trials differed in time since ITP diagnosis: at least 6 months versus at least 12 months. During the trials, doses could be increased every 2 weeks to a maximum of 75 mg once daily. The dose of PROMACTA was reduced if the platelet count exceeded 200 x 10^9/L and interrupted and reduced if it exceeded 400 x 10^9/L.

In the PETIT2 study (NCT01520909), patients refractory or relapsed to at least one prior ITP therapy with a platelet count less than 30 x 10^9/L (n = 92) were stratified by age and randomized (2:1) to PROMACTA (n = 63) or placebo (n = 29). The starting dose for patients aged 6 to 17 years was 50 mg once daily for those at least 27 kg and 37.5 mg once daily for those less than 27 kg, administered as oral tablets. A reduced dose of 25 mg once daily was used for East-/Southeast-Asian patients aged 6 to 17 years regardless of weight. The starting dose for patients aged 1 to 5 years was 1.2 mg/kg once daily (0.8 mg/kg once daily for East-/Southeast-Asian patients) administered as oral suspension.

The 13-week, randomized, double-blind period was followed by a 24-week, open-label period where patients from both arms were eligible to receive PROMACTA.

The median age of the patients was 9 years and 48% were female. Approximately 62% of patients had a baseline platelet count less than or equal to 15 x 10^9/L, a characteristic that was similar between treatment arms. The percentage of patients with at least 2 prior ITP therapies (predominantly corticosteroids and immunoglobulins) was 73% in the group treated with PROMACTA and 90% in the group treated with placebo. Four patients in the group treated with PROMACTA had undergone splenectomy.

The efficacy of PROMACTA in this trial was evaluated by the proportion of subjects on PROMACTA achieving platelet counts ≥ 50 x 10^9/L (in the absence of rescue therapy) for at least 6 out of 8 weeks between Weeks 5 to 12 of the randomized, double-blind period (Table 18).

Table 18. PETIT2: Platelet Count Response (≥ 50 x 10^9/L Without Rescue) for 6 out of 8 Weeks (between Weeks 5 to 12) Overall and by Age Cohort in Pediatric Patients 1 Year and Older With Chronic Immune Thrombocytopenia
Age cohort | PROMACTA | Placebo
Overall | 26/63 (41%)a | 1/29 (3%)
12 to 17 years | 10/24 (42%) | 1/10 (10%)
6 to 11 years | 11/25 (44%) | 0/13 (0%)
1 to 5 years | 5/14 (36%) | 0/6 (0%)
a p-value = < 0.001 for PROMACTA versus placebo.

More pediatric patients treated with PROMACTA (75%) compared with placebo (21%) had at least one platelet count greater than or equal to 50 x 10^9/L during the first 12 weeks of randomized treatment in absence of rescue therapy. Fewer pediatric patients treated with PROMACTA required rescue treatment during the randomized, double-blind period compared with placebo-treated patients (19% [12/63] versus 24% [7/29]). In the patients who achieved a platelet response (≥ 50 x 10^9/L without rescue) for 6 out of 8 weeks (between weeks 5 to 12), 62% (16/26) had an initial response in the first 2 weeks after starting PROMACTA.

Patients were permitted to reduce or discontinue baseline ITP therapy only during the open-label phase of the trial. Among 15 patients receiving other ITP therapy at baseline, 53% (8/15) reduced (n = 1) or discontinued (n = 7) concomitant therapy, mainly corticosteroids, without needing rescue therapy.

In the PETIT study (NCT00908037), patients refractory or relapsed to at least one prior ITP therapy with a platelet count less than 30 x 10^9/L (n = 67) were stratified by age and randomized (2:1) to PROMACTA (n = 45) or placebo (n = 22). Approximately 15% of patients met the definition of persistent ITP. The starting dose for patients aged 12 to 17 years was 37.5 mg once daily regardless of weight or race. The starting dose for patients aged 6 to 11 years was 50 mg once daily for those greater than or equal to 27 kg and 25 mg once daily for those less than 27 kg, administered as oral tablets. Reduced doses of 25 mg (for those greater than or equal to 27 kg) and 12.5 mg (for those less than 27 kg), each once daily, were used for East-/Southeast-Asian patients in this age range. The starting dose for patients aged 1 to 5 years was 1.5 mg/kg once daily (0.8 mg/kg once daily for East-/Southeast-Asian patients) administered as oral suspension.

The 7-week, randomized, double-blind period was followed by an open-label period of up to 24 weeks where patients from both arms were eligible to receive PROMACTA.

The median age of the patients was 10 years and 60% were female. Approximately 51% of patients had a baseline platelet count less than or equal to 15 x 10^9/L. The percentage of patients with at least 2 prior ITP therapies (predominantly corticosteroids and immunoglobulins) was 84% in the group treated with PROMACTA and 86% in the group treated with placebo. Five patients in the group treated with PROMACTA had undergone splenectomy.

The efficacy of PROMACTA in this trial was evaluated by the proportion of patients achieving platelet counts greater than or equal to 50 x 10^9/L (in absence of rescue therapy) at least once between Weeks 1 and 6 of the randomized, double-blind period (Table 19). Platelet response to PROMACTA was consistent across the age cohorts.

Table 19. PETIT: Platelet Count Response (≥ 50 x 10^9/L Without Rescue) Rates in Pediatric Patients 1 Year and Older With Persistent or Chronic Immune Thrombocytopenia
Age cohort | PROMACTA | Placebo
Overall | 28/45 (62%)a | 7/22 (32%)
12 to 17 years | 10/16 (62%) | 0/8 (0%)
6 to 11 years | 12/19 (63%) | 3/9 (33%)
1 to 5 years | 6/10 (60%) | 4/5 (80%)
a p-value = 0.011 for PROMACTA versus placebo.

Fewer pediatric patients treated with PROMACTA required rescue treatment during the randomized, double-blind period compared with placebo-treated patients (13% [6/45] versus 50% [11/22]).

Patients were permitted to reduce or discontinue baseline ITP therapy only during the open-label phase of the trial. Among 13 patients receiving other ITP therapy at baseline, 46% (6/13) reduced (n = 3) or discontinued (n = 3) concomitant therapy, mainly corticosteroids, without needing rescue therapy.

14.2 Chronic Hepatitis C-Associated Thrombocytopenia

The efficacy and safety of PROMACTA for the treatment of thrombocytopenia in adult patients with chronic hepatitis C were evaluated in two randomized, double-blind, placebo-controlled trials. The ENABLE1 study (NCT00516321) utilized peginterferon alfa-2a (PEGASYS®) plus ribavirin for antiviral treatment and the ENABLE2 study (NCT00529568) utilized peginterferon alfa-2b (PEGINTRON®) plus ribavirin. In both trials, patients with a platelet count of less than 75 x 10^9/L were enrolled and stratified by platelet count, screening HCV RNA, and HCV genotype. Patients were excluded if they had evidence of decompensated liver disease with Child-Pugh score greater than 6 (class B and C), history of ascites, or hepatic encephalopathy. The median age of the patients in both trials was 52 years, 63% were male, and 74% were Caucasian. Sixty-nine percent of patients had HCV genotypes 1, 4, 6, with the remainder genotypes 2 and 3. Approximately 30% of patients had been previously treated with interferon and ribavirin. The majority of patients (90%) had bridging fibrosis and cirrhosis, as indicated by noninvasive testing. A similar proportion (95%) of patients in both treatment groups had Child-Pugh class A (score 5 to 6) at baseline. A similar proportion of patients (2%) in both treatment groups had baseline international normalized ratio (INR) greater than 1.7. Median baseline platelet counts (approximately 60 x 10^9/L) were similar in both treatment groups. The trials consisted of 2 phases – a pre-antiviral treatment phase and an antiviral treatment phase. In the pre-antiviral treatment phase, patients received open-label PROMACTA to increase the platelet count to a threshold of greater than or equal to 90 x 10^9/L for ENABLE1 and greater than or equal to 100 x 10^9/L for ENABLE2. PROMACTA was administered at an initial dose of 25 mg once daily for 2 weeks and increased in 25-mg increments over 2- to 3-week periods to achieve the optimal platelet count to initiate antiviral therapy. The maximal time patients could receive open-label PROMACTA was 9 weeks. If threshold platelet counts were achieved, patients were randomized (2:1) to the same dose of PROMACTA at the end of the pre-treatment phase or to placebo. PROMACTA was administered in combination with pegylated interferon and ribavirin per their respective prescribing information for up to 48 weeks.

The efficacy of PROMACTA for both trials was evaluated by sustained virologic response (SVR) defined as the percentage of patients with undetectable HCV-RNA at 24 weeks after completion of antiviral treatment. The median time to achieve the target platelet count greater than or equal to 90 x 10^9/L was approximately 2 weeks. Ninety-five percent of patients were able to initiate antiviral therapy.

In both trials, a significantly greater proportion of patients treated with PROMACTA achieved SVR (see Table 20). The improvement in the proportion of patients who achieved SVR was consistent across subgroups based on baseline platelet count (less than 50 x 10^9/L versus greater than or equal to 50 x 10^9/L). In patients with high baseline viral loads (greater than or equal to 800,000), the SVR rate was 18% (82/452) for PROMACTA versus 8% (20/239) for placebo.

Table 20. ENABLE1 and ENABLE2: Sustained Virologic Response (SVR) in Adults With Chronic Hepatitis C
 | ENABLE1a |  | ENABLE2b
Pre-antiviral treatment phase | n = 715 |  | n = 805
% Patients who achieved target platelet counts and initiated antiviral therapyc | 95% |  | 94%
Antiviral treatment phase | PROMACTA; n = 450; % | Placebo; n = 232; % | PROMACTA; n = 506; % | Placebo; n = 253; %
Overall SVRd | 23 | 14 | 19 | 13
HCV genotype 2, 3 | 35 | 24 | 34 | 25
HCV genotype 1, 4, 6 | 18 | 10 | 13 | 7
Abbreviation: HCV, hepatitis C virus.
aPROMACTA given in combination with peginterferon alfa-2a (180 mcg once weekly for 48 weeks for genotypes 1/4/6; 24 weeks for genotype 2 or 3) plus ribavirin (800 to 1,200 mg daily in 2 divided doses orally).
bPROMACTA given in combination with peginterferon alfa-2b (1.5 mcg/kg once weekly for 48 weeks for genotypes 1/4/6; 24 weeks for genotype 2 or 3) plus ribavirin (800 to 1,400 mg daily in 2 divided doses orally).
cTarget platelet count was ≥ 90 x 10^9/L for ENABLE1 and ≥ 100 x 10^9/L for ENABLE2.
d p-value < 0.05 for PROMACTA versus placebo.

The majority of patients treated with PROMACTA (76%) maintained a platelet count greater than or equal to 50 x 10^9/L compared with 19% for placebo. A greater proportion of patients on PROMACTA did not require any antiviral dose reduction as compared with placebo (45% versus 27%).

14.3 Severe Aplastic Anemia

First-Line Treatment of Severe Aplastic Anemia

PROMACTA in combination with h-ATG and cyclosporine was investigated in a single-arm, single-center, open-label sequential cohort trial (Study ETB115AUS01T, referred to as Study US01T [NCT01623167]) in patients with severe aplastic anemia who had not received prior immunosuppressive therapy (IST) with any ATG, alemtuzumab, or high dose cyclophosphamide. A total of 153 patients received PROMACTA in Study US01T in three sequential cohorts and an extension of the third cohort. The multiple cohorts received the same PROMACTA starting dose but differed by treatment start day and duration. The starting dose of PROMACTA for patients 12 years and older was 150 mg once daily (a reduced dose of 75 mg was administered for East-/Southeast-Asians), 75 mg once daily for pediatric patients aged 6 to 11 years (a reduced dose of 37.5 mg was administered for East-/Southeast-Asians), and 2.5 mg/kg once daily for pediatric patients aged 2 to 5 years (a reduced dose of 1.25 mg/kg was administered for East-/Southeast-Asians).

- Cohort 1 (n = 30): PROMACTA on Day 14 to Month 6 (D14-M6) plus h-ATG and cyclosporine
- Cohort 2 (n = 31): PROMACTA on Day 14 to Month 3 (D14-M3) plus h-ATG and cyclosporine
- Cohort 3 + Extension cohort [PROMACTA D1-M6 cohort] (n = 92): PROMACTA on Day 1 to Month 6 (D1-M6) plus h-ATG and cyclosporine (with all patients eligible to receive low dose of cyclosporine (maintenance dose) if they achieved a hematologic response at 6 months)

PROMACTA dose reductions were conducted for elevated platelet counts and hepatic impairment. Table 21 includes the dosages of h-ATG and cyclosporine administered in combination with PROMACTA in Study US01T.

Data from the Cohort 3 + Extension cohort support the efficacy of PROMACTA for the first-line treatment of patients with severe aplastic anemia (Table 22). The results presented in this section represent the findings from the Cohort 3 and Extension cohort (n = 92).

Table 21. Dosages of Immunosuppressive Therapy Administered With PROMACTA in Study US01T
Agent | Dose Administered in the Pivotal Trial
Horse antithymocyte globulin (h-ATG) | 40 mg/kg/day, based on actual body weight, administered intravenously on Days 1 to 4 of the 6-month treatment period
Cyclosporinea (therapeutic dose for 6 months, from Day 1 to Month 6, adjusted to obtain a target therapeutic trough level between 200 mcg/L and 400 mcg/L) | Patients 12 years and older (total daily dose of 6 mg/kg/day); 3 mg/kg, based on actual body weight, orally every 12 hours for 6 months, starting on Day 1; Patients > 20 years of age with a body mass index > 35 or patients 12 to 20 years of age with a body mass index > 95th percentile:; 3 mg/kg, based on adjusted body weightb, orally every 12 hours for 6 months, starting on Day 1; Patients 2 to 11 years of age (total daily dose of 12 mg/kg/day); 6 mg/kg, based on actual body weight, orally every 12 hours for 6 months, starting on Day 1; Patients 2 to 11 years of age with a body mass index > 95th percentile:; 6 mg/kg, based on adjusted body weightb, orally every 12 hours for 6 months, starting on Day 1
Cyclosporine (maintenance dose, from Month 6 to Month 24) | For patients who achieve a hematologic response at 6 months; 2 mg/kg/day administered orally at a fixed dose for an additional 18 months
aDose of cyclosporine was adjusted to achieve the above recommended target trough levels; refer to the appropriate cyclosporine prescribing information.
bCalculated as the midpoint between the ideal body weight and actual body weight.

In the PROMACTA D1-M6 cohort, the median age was 28 years (range, 5 to 82 years) with 16% and 28% of patients ≥ 65 years of age and < 17 years of age, respectively. Forty-six percent of patients were male and the majority of patients were White (62%). Patients weighing 12 kg or less or patients with ALT or AST > 5x upper limit of normal were excluded from the trial.

The efficacy of PROMACTA in combination with h-ATG and cyclosporine was established on the basis of complete hematological response at 6 months. A complete response was defined as hematological parameters meeting all 3 of the following values on 2 consecutive serial blood count measurements at least one week apart: absolute neutrophil count (ANC) > 1000/mcL, platelet count > 100 x 10^9/L and hemoglobin > 10 g/dL. A partial response was defined as blood counts no longer meeting the standard criteria for severe pancytopenia in severe aplastic anemia equivalent to 2 of the following values on 2 consecutive serial blood count measurements at least one week apart: ANC > 500/mcL, platelet count > 20 x 10^9/L, or reticulocyte count > 60,000/mcL. Overall response rate is defined as the number of partial responses plus complete responses.

Table 22. Study US01T: Hematologic Response in First-Line Treatment of Patients With Severe Aplastic Anemia
 | PROMACTA D1-M6 + h-ATG + cyclosporine n = 92
Month 6, na; Overall response, n (%) [95% CI]; Complete response, n (%) [95% CI] | 87 69 (79) [69, 87] 38 (44) [33, 55]
Median duration of overall response, nb | 70
Months (95% CI) | 24.3 (21.4, NE)
Median duration of complete response, nb | 46
Months (95% CI) | 24.3 (23.0, NE)
Abbreviation: NE, not estimable.
aThe number of patients who reached the 6-month assessment or withdrew earlier is the denominator for percentage calculation.
bNumber of responders at any time.

The overall and complete hematological response rates at Year 1 (n = 78) are 56.4% and 38.5% and at Year 2 (n = 62) are 38.7% and 30.6%, respectively.

Pediatric Patients

Thirty-four patients 2 to 16 years of age were enrolled in Study US01T. In the D1-M6 cohort, 7 and 17 out of 25 pediatric patients achieved a complete and overall response, respectively, at 6 months.

Refractory Severe Aplastic Anemia

PROMACTA was studied in a single-arm, single-center, open-label trial (Study ETB115AUS28T, referred to as Study US28T [NCT00922883]) in 43 patients with severe aplastic anemia who had an insufficient response to at least one prior immunosuppressive therapy and who had a platelet count less than or equal to 30 x 10^9/L. PROMACTA was administered at an initial dose of 50 mg once daily for 2 weeks and increased over 2-week periods up to a maximum dose of 150 mg once daily. The efficacy of PROMACTA in the study was evaluated by the hematologic response assessed after 12 weeks of treatment. Hematologic response was defined as meeting 1 or more of the following criteria: 1) platelet count increases to 20 x 10^9/L above baseline, or stable platelet counts with transfusion independence for a minimum of 8 weeks; 2) hemoglobin increase by greater than 1.5 g/dL, or a reduction in greater than or equal to 4 units of red blood cell (RBC) transfusions for 8 consecutive weeks; 3) ANC increase of 100% or an ANC increase greater than 0.5 x 10^9/L. PROMACTA was discontinued after 16 weeks if no hematologic response was observed. Patients who responded continued therapy in an extension phase of the trial.

The treated population had median age of 45 years (range, 17 to 77 years) and 56% were male. At baseline, the median platelet count was 20 x 10^9/L, hemoglobin was 8.4 g/dL, ANC was 0.58 x 10^9/L, and absolute reticulocyte count was 24.3 x 10^9/L. Eighty-six percent of patients were red blood cell (RBC) transfusion dependent and 91% were platelet transfusion dependent. The majority of patients (84%) received at least 2 prior immunosuppressive therapies. Three patients had cytogenetic abnormalities at baseline.

Table 23 presents the efficacy results.

Table 23. Study US28T: Hematologic Response in Patients With Refractory Severe Aplastic Anemia
Outcome | PROMACTA; n = 43
Response ratea, n (%); 95% CI (%) | 17 (40); (25, 56)
Median of duration of response in months (95% CI) | NRb (3.0, NRb)
aIncludes single- and multi-lineage.
bNR = not reached due to few events (relapsed).

In the 17 responders, the platelet transfusion-free period ranged from 8 to 1096 days with a median of 200 days, and the RBC transfusion-free period ranged from 15 to 1082 days with a median of 208 days.

In the extension phase, 8 patients achieved a multi-lineage response; 4 of these patients subsequently tapered off treatment with PROMACTA and maintained the response (median follow-up: 8.1 months, range, 7.2 to 10.6 months).

16 HOW SUPPLIED/STORAGE AND HANDLING

16.1 Tablets

- The 12.5 mg tablets are round, biconvex, white, film-coated tablets debossed with “GS MZ1” and 12.5 on one side and are available in bottles of 30: NDC 0078-0684-15
- The 25 mg tablets are round, biconvex, orange, film-coated tablets debossed with “GS NX3” and 25 on one side and are available in bottles of 30: NDC 0078-0685-15
- The 50 mg tablets are round, biconvex, blue, film-coated tablets debossed with “GS UFU” and 50 on one side and are available:
  - Bottles of 14 NDC 0078-0686-55
  - Bottles of 30 NDC 0078-0686-15
- The 75 mg tablets are round, biconvex, pink, film-coated tablets debossed with “GS FFS” and 75 on one side and are available in bottles of 30: NDC 0078-0687-15

Store at room temperature between 20°C to 25°C (68°F to 77°F); excursions permitted between 15°C and 30°C (59°F and 86°F) [see USP Controlled Room Temperature]. Dispense in original bottle.

16.2 For Oral Suspension

- The 12.5 mg for oral suspension is a reddish-brown to yellow powder in unit-dose packets, copackaged in a kit with a 40 mL reconstitution vessel, a threaded closure with syringe-port capability, and 30 single-use oral dosing syringes.

Each kit (NDC 0078-0972-61) contains 30 packets: NDC 0078-0972-19

- The 25 mg for oral suspension is a reddish-brown to yellow powder in unit-dose packets, copackaged in a kit with a 40 mL reconstitution vessel, a threaded closure with syringe-port capability, and 30 single-use oral dosing syringes.

Each kit (NDC 0078-0697-61) contains 30 packets: NDC 0078-0697-19

Store at room temperature between 20°C to 25°C (68°F to 77°F); excursions permitted between 15°C and 30°C (59°F and 86°F) [see USP Controlled Room Temperature]. Following reconstitution, the product should be administered immediately but may be stored for a maximum period of 30 minutes between 20°C to 25°C (68°F to 77°F); excursions permitted between 15°C and 30°C (59°F and 86°F) [see USP Controlled Room Temperature]. Throw away (discard) the mixture if not used within 30 minutes.

17 PATIENT COUNSELING INFORMATION

Advise the patient or caregiver to read the FDA-approved patient labeling (Medication Guide and Instructions for Use).

Prior to treatment, patients should fully understand and be informed of the following risks and considerations for PROMACTA:

Risks

Hepatotoxicity

- Therapy with PROMACTA may be associated with hepatobiliary laboratory abnormalities [see Warnings and Precautions (5.2)].
- Advise patients with chronic hepatitis C and cirrhosis that they may be at risk for hepatic decompensation when receiving PROMACTA with alfa interferon therapy [see Warnings and Precautions (5.1)].
- Advise patients that they should report any of the following signs and symptoms of liver problems to their healthcare provider right away [see Warnings and Precautions (5.2)].
  - yellowing of the skin or the whites of the eyes (jaundice)
  - unusual darkening of the urine
  - unusual tiredness
  - right upper stomach area pain
  - confusion
  - swelling of the stomach area (abdomen)

Risk of Bleeding Upon PROMACTA Discontinuation

- Advise patients that thrombocytopenia and risk of bleeding may reoccur upon discontinuing PROMACTA, particularly if PROMACTA is discontinued while the patient is on anticoagulants or antiplatelet agents. Advise patients that during therapy with PROMACTA, they should continue to avoid situations or medications that may increase the risk for bleeding.

Thrombotic/Thromboembolic Complications

- Advise patients that too much PROMACTA may result in excessive platelet counts and a risk for thrombotic/thromboembolic complications [see Warnings and Precautions (5.4)].

Cataracts

- Advise patients to have a baseline ocular examination prior to administration of PROMACTA and be monitored for signs and symptoms of cataracts during therapy [see Warnings and Precautions (5.5)].

Drug Interactions

- Advise patients to take PROMACTA at least 2 hours before or 4 hours after calcium-rich foods, mineral supplements, and antacids which contain polyvalent cations, such as iron, calcium, aluminum, magnesium, selenium, and zinc [see Dosage and Administration (2.4), Drug Interactions (7.1)].

Lactation

- Advise women not to breastfeed during treatment with PROMACTA [see Use in Specific Populations (8.2)].

Administration of PROMACTA

- For patients with persistent or chronic ITP, therapy with PROMACTA is administered to achieve and maintain a platelet count greater than or equal to 50 x 10^9/L as necessary to reduce the risk for bleeding [see Indications and Usage (1.1)].
- For patients with chronic hepatitis C, therapy with PROMACTA is administered to achieve and maintain a platelet count necessary to initiate and maintain antiviral therapy with pegylated interferon and ribavirin [see Indications and Usage (1.2)].
- Advise patients to take PROMACTA without a meal or with a meal low in calcium (≤ 50 mg) and at least 2 hours before or 4 hours after other medications (e.g., antacids) and calcium-rich foods [see Dosage and Administration (2.4)].
- Prior to use of the oral suspension, ensure patients or caregivers receive training on proper dosing, preparation, and administration [see Dosage and Administration (2.4)].
- Inform patients or caregivers how many packets to administer to get the full dose [see Instructions for Use].
- Inform patients or caregivers to use a new oral dosing syringe to prepare each dose of PROMACTA for oral suspension [see Instructions for Use].

The following are registered trademarks of their respective owners: PEGASYS/Hoffmann-La Roche Inc.; PEGINTRON/Schering Corporation.

Distributed by:
Novartis Pharmaceuticals Corporation
East Hanover, New Jersey 07936

© Novartis

T2025-27

MEDICATION GUIDE

PROMACTA® (pro-MAC-ta)
(eltrombopag)
tablets

PROMACTA® (pro-MAC-ta)
(eltrombopag)
for oral suspension

What is the most important information I should know about PROMACTA?
PROMACTA can cause serious side effects, including:
Liver problems:

- If you have chronic hepatitis C virus and take PROMACTA with interferon and ribavirin treatment, PROMACTA may increase your risk of liver problems. If your healthcare provider tells you to stop your treatment with interferon and ribavirin, you will also need to stop taking PROMACTA.
- PROMACTA may increase your risk of liver problems that may be severe and possibly life threatening. Your healthcare provider will do blood tests to check your liver function before you start taking PROMACTA and during your treatment. Your healthcare provider may stop your treatment with PROMACTA if you have changes in your liver function blood tests.

Tell your healthcare provider right away if you have any of these signs and symptoms of liver problems:

- yellowing of the skin or the whites of the eyes (jaundice)
- unusual darkening of the urine
- unusual tiredness

- right upper stomach area (abdomen) pain
- confusion
- swelling of the stomach area (abdomen)

See “What are the possible side effects of PROMACTA?” for other side effects of PROMACTA.

What is PROMACTA?
PROMACTA is a prescription medicine used to treat adults and children 1 year of age and older with low blood platelet counts due to persistent or chronic immune thrombocytopenia (ITP), when other medicines to treat ITP or surgery to remove the spleen have not worked well enough.

PROMACTA is also used to treat people with:

- low blood platelet counts due to chronic hepatitis C virus (HCV) infection before and during treatment with interferon.
- severe aplastic anemia (SAA) in combination with other medicines to treat SAA, as the first treatment for adults and children 2 years of age and older.
- severe aplastic anemia (SAA) when other medicines to treat SAA have not worked well enough.

PROMACTA is used to try to raise platelet counts in order to lower your risk for bleeding.

PROMACTA is not used to make platelet counts normal.

PROMACTA is not for use in people with a pre-cancerous condition called myelodysplastic syndrome (MDS), or in people with low platelet counts caused by certain other medical conditions or diseases.

It is not known if PROMACTA is safe and effective when used with other antiviral medicines to treat chronic hepatitis C.

It is not known if PROMACTA is safe and effective in children:

- younger than 1 year with ITP
- with low blood platelet counts due to chronic hepatitis C
- whose severe aplastic anemia (SAA) has not improved after previous treatments
- younger than 2 years when used in combination with other medicines to treat SAA as the first treatment for SAA

Before you take PROMACTA, tell your healthcare provider about all of your medical conditions, including if you:

- have liver problems
- have a precancerous condition called MDS or a blood cancer
- have or had a blood clot
- have a history of cataracts
- have had surgery to remove your spleen (splenectomy)
- have bleeding problems
- are of East-/Southeast-Asian ancestry. You may need a lower dose of PROMACTA
- are pregnant or plan to become pregnant. It is not known if PROMACTA will harm an unborn baby. Tell your healthcare provider if you become pregnant or think you may be pregnant during treatment with PROMACTA.
  - Females who are able to become pregnant, should use effective birth control (contraception) during treatment with PROMACTA and for at least 7 days after stopping treatment with PROMACTA. Talk to your healthcare provider about birth control methods that may be right for you during this time.
- are breastfeeding or plan to breastfeed. You should not breastfeed during your treatment with PROMACTA. Talk to your healthcare provider about the best way to feed your baby during this time.
- Tell your healthcare provider about all the medicines you take, including prescription and over-the-counter medicines, vitamins, and herbal supplements. PROMACTA may affect the way certain medicines work. Certain other medicines may affect the way PROMACTA works.

Especially tell your healthcare provider if you take:

- certain medicines used to treat high cholesterol, called “statins”
- a blood thinner medicine

Certain medicines may keep PROMACTA from working correctly. Take PROMACTA at least 2 hours before or 4 hours after taking these products:

- antacid medicine used to treat stomach ulcers or heartburn
- multivitamins or products that contain iron, calcium, aluminum, magnesium, selenium, and zinc which may be found in mineral supplements

Ask your healthcare provider if you are not sure if your medicine is one that is listed above.
Know the medicines you take. Keep a list of them and show it to your healthcare provider and pharmacist when you get a new medicine.

How should I take PROMACTA?

- Take PROMACTA exactly as your healthcare provider tells you to take it. Your healthcare provider will prescribe the dose of PROMACTA tablets or PROMACTA for oral suspension that is right for you.
- If your healthcare provider prescribes PROMACTA tablets, take PROMACTA tablets whole. Do not split, chew, or crush PROMACTA tablets and do not mix with food or liquids.
- If your healthcare provider prescribes PROMACTA for oral suspension, see the “Instructions for Use” that comes with your medicine for instructions on how to correctly mix and take a dose of PROMACTA.
- Use a new single-use oral dosing syringe to prepare each dose of PROMACTA for oral suspension. Do not re-use the oral dosing syringe.
- Do not stop taking PROMACTA without talking with your healthcare provider first. Do not change your dose or schedule for taking PROMACTA unless your healthcare provider tells you to change it.
- Take PROMACTA without a meal or with a meal low in calcium (50 mg or less) and at least 2 hours before or 4 hours after eating calcium-rich foods, such as dairy products, calcium-fortified juices, and certain fruits and vegetables.
- If you miss a dose of PROMACTA, wait and take your next scheduled dose. Do not take more than 1 dose of PROMACTA in 1 day.
- If you take too much PROMACTA, you may have a higher risk of serious side effects. Call your healthcare provider right away.
- Your healthcare provider will check your platelet count during your treatment with PROMACTA and change your dose of PROMACTA as needed.
- Tell your healthcare provider about any bruising or bleeding that happens while you take and after you stop taking PROMACTA.
- If you have SAA, your healthcare provider may do tests to monitor your bone marrow during treatment with PROMACTA.

What should I avoid while taking PROMACTA?
Avoid situations and medicines that may increase your risk of bleeding.

What are the possible side effects of PROMACTA?
PROMACTA may cause serious side effects, including:

- See “What is the most important information I should know about PROMACTA?”
- Increased risk of worsening of a precancerous blood condition called myelodysplastic syndrome (MDS) to acute myelogenous leukemia (AML). PROMACTA is not for use in people with a precancerous condition called myelodysplastic syndromes (MDS). See “What is PROMACTA?” If you have MDS and receive PROMACTA, you have an increased risk that your MDS condition may worsen and become a blood cancer called AML. If your MDS worsens to become AML, you may have an increased risk of death from AML.
- High platelet counts and higher risk for blood clots. Your risk of getting a blood clot is increased if your platelet count is too high during treatment with PROMACTA. Your risk of getting a blood clot may also be increased during treatment with PROMACTA if you have normal or low platelet counts. You may have severe problems or die from some forms of blood clots, such as clots that travel to the lungs or that cause heart attacks or strokes. Your healthcare provider will check your blood platelet counts, and change your dose or stop PROMACTA if your platelet counts get too high. Tell your healthcare provider right away if you have signs and symptoms of a blood clot in the leg, such as swelling, pain, or tenderness in your leg.
  People with chronic liver disease may be at risk for a type of blood clot in the stomach area (abdomen). Tell your healthcare provider right away if you have stomach-area (abdomen) pain, nausea, vomiting, or diarrhea as these may be symptoms of this type of blood clot.
- New or worsened cataracts (a clouding of the lens in the eye). New or worsened cataracts can happen in people taking PROMACTA. Your healthcare provider will check your eyes before and during your treatment with PROMACTA. Tell your healthcare provider about any changes in your eyesight while taking PROMACTA.

The most common side effects of PROMACTA in adults and children include:

- low red blood cell count (anemia)
- nausea
- fever
- abnormal liver function tests

- cough
- tiredness
- headache
- diarrhea

Laboratory tests may show abnormal changes to the cells in your bone marrow.
Tell your healthcare provider if you have any side effect that bothers you or that does not go away. These are not all of the possible side effects of PROMACTA. For more information, ask your healthcare provider or pharmacist.
Call your doctor for medical advice about side effects. You may report side effects to FDA at 1-800-FDA-1088.

How should I store PROMACTA tablets and PROMACTA for oral suspension?
Tablets:

- Store PROMACTA tablets at room temperature between 68°F to 77°F (20°C to 25°C).
- Keep PROMACTA in the bottle given to you.

For oral suspension:

- Store PROMACTA for oral suspension at room temperature between 68°F to 77°F (20°C to 25°C).
- After mixing, PROMACTA should be taken right away but may be stored for no more than 30 minutes between 68°F to 77°F (20°C to 25°C). Throw away (discard) the mixture if not used within 30 minutes.

Keep PROMACTA and all medicines out of the reach of children.

General information about the safe and effective use of PROMACTA
Medicines are sometimes prescribed for purposes other than those listed in a Medication Guide. Do not use PROMACTA for a condition for which it was not prescribed. Do not give PROMACTA to other people, even if they have the same symptoms that you have. It may harm them.
You can ask your healthcare provider or pharmacist for information about PROMACTA that is written for health professionals.

What are the ingredients in PROMACTA?
Tablets
Active ingredient: eltrombopag olamine
Inactive ingredients:

- Tablet Core: magnesium stearate, mannitol, microcrystalline cellulose, povidone, and sodium starch glycolate.
  - Coating: FD&C Blue No. 2 aluminum lake (50-mg tablet), FD&C Yellow No. 6 aluminum lake (25-mg tablet), hypromellose, Iron Oxide Black and Iron Oxide Red (75-mg tablet), polyethylene glycol 400, polysorbate 80 (12.5-mg tablet), or titanium dioxide.

For oral suspension
Active ingredient: eltrombopag olamine
Inactive ingredients: mannitol, sucralose, and xanthan gum
Distributed by: Novartis Pharmaceuticals Corporation, East Hanover, New Jersey 07936
© Novartis
For more information about PROMACTA call 1-888-669-6682.

This Medication Guide has been approved by the U.S. Food and Drug Administration

Revised: June 2025

T2025-28

INSTRUCTIONS FOR USE

PROMACTA® [pro-MAC-ta]

(eltrombopag)

for oral suspension

Read all the Instructions for Use and follow the steps below to mix and give a dose of PROMACTA for oral suspension.

Important information you need to know before taking PROMACTA for oral suspension:

- Do not take PROMACTA for oral suspension or give it to someone else until you have been shown how to properly mix and give a dose of PROMACTA for oral suspension. Your healthcare provider or nurse will show you how to mix and give a dose of PROMACTA for oral suspension properly.
- PROMACTA for oral suspension must be mixed with cool or cold water only. Do not use hot water to prepare the oral suspension.
- Give the dose of suspension right away after mixing with water. If the medicine is not given within 30 minutes, you will have to mix a new dose. Throw away (discard) the unused mixture into the trash. Do not pour it down the drain.
- If PROMACTA for oral suspension comes in contact with your skin, wash the skin right away with soap and water. Call your healthcare provider if you have a skin reaction or if you have any questions. If you spill any powder or liquid, follow the clean-up instructions in Step 12.
- Contact your healthcare provider or pharmacist if you have any questions about how to mix or give PROMACTA to your child, or if you damage or lose any of the supplies in your kit.
- Do not re-use the oral dosing syringe. Use a new single-use oral dosing syringe to prepare each dose of PROMACTA for oral suspension.
- After you have used all 30 packets, throw all the remaining supplies (mixing bottle, lid with cap, and oral dosing syringe) away in the trash.

Each PROMACTA for oral suspension kit contains the following supplies:

30 packets of PROMACTA for oral suspension

1 Reusable mixing bottle with lid and cap

30 Single-use 20 mL oral dosing syringes (Use a new (single-use) oral dosing syringe to prepare each dose of PROMACTA for oral suspension)

You will need the following to give a dose of PROMACTA for oral suspension.

From the kit:

- prescribed number of packets
- 1 reusable mixing bottle with lid and cap. Note: Due to its small size, the cap may pose a danger of choking to small children.
- 1 single-use 20 mL oral dosing syringe (Use a new (single-use) oral dosing syringe to prepare each dose of PROMACTA for oral suspension)

Not included in the kit:

- 1 clean glass or cup filled with drinking water
- scissors to cut packet
- paper towels or disposable cloth
- disposable gloves (optional)

How do I prepare a dose of PROMACTA for oral suspension?

Step 1. Make sure that the mixing bottle, cap, lid and oral dosing syringe are dry before use. Remove the lid from the mixing bottle.

- Prepare a clean, flat work surface.
- Wash and dry your hands before preparing the medicine.

Step 2. Fill the oral dosing syringe with 20 mL of drinking water from the glass or cup.

- Start with the plunger pushed all the way into the syringe.
- Place the tip of the oral dosing syringe all the way into the water and pull back on the plunger to the 20 mL mark on the barrel of the oral dosing syringe.

Note: Use a new (single-use) oral dosing syringe to prepare each dose of PROMACTA for oral suspension.

Figure 1.

Step 3. Place the tip of the oral dosing syringe into the open mixing bottle. Empty water into open mixing bottle by slowly pushing the plunger all the way into the oral dosing syringe.

Figure 2.

Step 4. Take only the prescribed number of packets for one dose out of the kit. You may need to use more than one packet to prepare the entire dose.

12.5 mg packets
Dose Number of 12.5 mg Packets Needed
12.5 mg dose 1 packet
25 mg dose 2 packets
50 mg dose 4 packets
75 mg dose 6 packets

25 mg packets
Dose Number of 25 mg Packets Needed
12.5 mg dose 1 packet (Note: See Step 9 for instructions on how to give a 12.5 mg dose using a 25 mg packet.)
25 mg dose 1 packet
50 mg dose 2 packets
75 mg dose 3 packets

Step 5. Add the prescribed number of packets to the mixing bottle.

- Tap the top of each packet to make sure the contents fall to the bottom.
- Cut off the top of the packet with scissors and empty the entire contents of the packet into the mixing bottle.
- Make sure not to spill the powder outside the mixing bottle.

Figure 3.

Step 6. Screw the lid tightly onto the mixing bottle. Make sure the cap is pushed onto the lid.

Step 7. Gently and slowly shake the mixing bottle back and forth for at least 20 seconds to mix the water with the powder.

- To prevent the mixture from foaming, do not shake the mixing bottle hard.

Figure 4.

How should I give a dose of PROMACTA for oral suspension?

Step 8. Make sure the plunger is pushed all the way into the oral dosing syringe. Pull cap off the mixing bottle lid and insert the tip of the oral dosing syringe into the hole in the lid.

Step 9. Transfer the mixture into the oral dosing syringe. The liquid will be dark brown in color.

- Turn the mixing bottle upside down along with the oral dosing syringe.
- Pull back the plunger:

12.5 mg packet
  - until all the medicine is in the oral dosing syringe (12.5 mg, 25 mg, 50 mg, or 75 mg dose)

25 mg packet
  - to the 10 mL mark on the oral dosing syringe for a 12.5 mg dose only
    OR
  - until all the medicine is in the oral dosing syringe (25 mg, 50 mg, or 75 mg dose).

Figure 5.

Step 10. Return the mixing bottle to the upright position and remove the oral dosing syringe from the mixing bottle.

Figure 6.

Step 11. Giving a dose of PROMACTA for oral suspension to a child.

- Place the tip of the oral dosing syringe into the inside of the child’s cheek.
- Slowly push the plunger all the way down to give the entire dose. Make sure the child has time to swallow the medicine.

Figure 7.

How should I clean up?

Step 12. Carefully clean up any spill of the powder or suspension with a damp paper towel or disposable cloth.

- To avoid possibly staining your skin, consider using disposable gloves.
- Throw away (discard) used paper towel or disposable cloth and gloves in the trash.

Step 13. Clean the mixing supplies.

- Do not reuse any of the mixture remaining in the mixing bottle.
- Throw away (discard) any mixture remaining in the mixing bottle in the trash. Do not pour down the drain.
- Throw away (discard) the used oral dosing syringe. Use a new (single-use) oral dosing syringe to prepare each dose of PROMACTA for oral suspension.
- Rinse the mixing bottle and lid under running water and air dry. The mixing bottle may become stained from the medicine. This is normal.
- Wash hands with soap and water.

How should I store PROMACTA for oral suspension?

- Store PROMACTA for oral suspension at room temperature between 68°F to 77°F (20°C to 25°C).
- After mixing, PROMACTA should be taken right away but may be stored for no more than 30 minutes between 68°F to 77°F (20°C to 25°C). Throw away (discard) the mixture if not used within 30 minutes.

Keep PROMACTA and all medicines out of the reach of children.

Distributed by:
Novartis Pharmaceuticals Corporation
East Hanover, New Jersey 07936

© Novartis

This Instructions for Use has been approved by the U.S. Food and Drug Administration.

Revised: June 2025

T2025-30

PRINCIPAL DISPLAY PANEL

NDC 0078-0684-15

Rx only

Promacta®
(eltrombopag) Tablets
12.5 mg

Swallow tablets whole. Do not
split, chew, or crush tablets.

Dispense with Medication Guide
attached or provided separately.

NOVARTIS

30 Tablets

PRINCIPAL DISPLAY PANEL

NDC 0078-0685-15

Rx only

Promacta®
(eltrombopag) Tablets
25 mg

Swallow tablets whole. Do not
split, chew, or crush tablets.

Dispense with Medication Guide
attached or provided separately.

NOVARTIS

30 Tablets

PRINCIPAL DISPLAY PANEL

NDC 0078-0686-15

Rx only

Promacta®
(eltrombopag) Tablets
50 mg

Swallow tablets whole. Do not
split, chew, or crush tablets.

Dispense with Medication Guide
attached or provided separately.

NOVARTIS

30 Tablets

PRINCIPAL DISPLAY PANEL

NDC 0078-0687-15

Rx only

Promacta®
(eltrombopag) Tablets
75 mg

Swallow tablets whole. Do not
split, chew, or crush tablets.

Dispense with Medication Guide
attached or provided separately.

NOVARTIS

30 Tablets

PRINCIPAL DISPLAY PANEL

NDC 0078-0972-61

Rx only

Promacta®
(eltrombopag)
for Oral Suspension

12.5 mg

Dispense with Medication Guide enclosed or provided separately.

30 Packets

NOVARTIS

PRINCIPAL DISPLAY PANEL

NDC 0078-0697-61

Rx only

Promacta®
(eltrombopag)
for Oral Suspension

25 mg

Dispense with Medication Guide enclosed or provided separately.

30 Packets

NOVARTIS